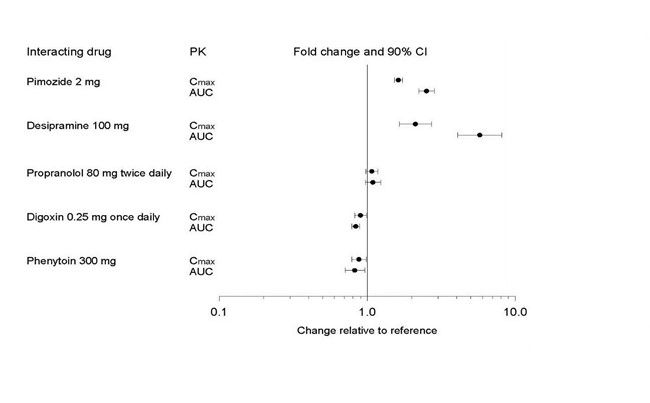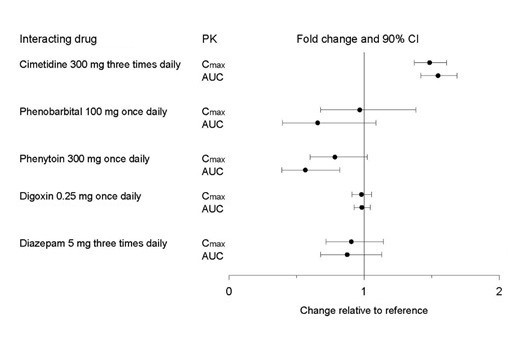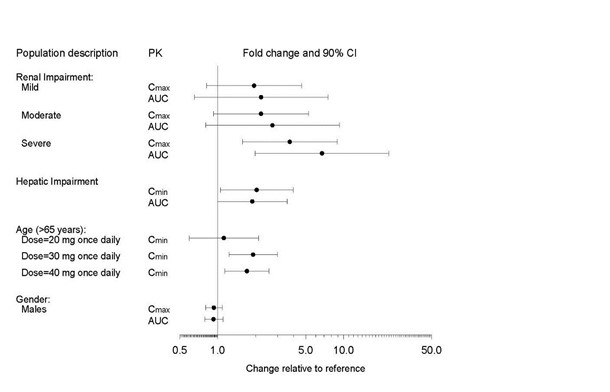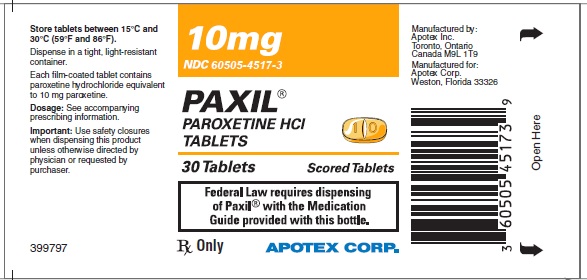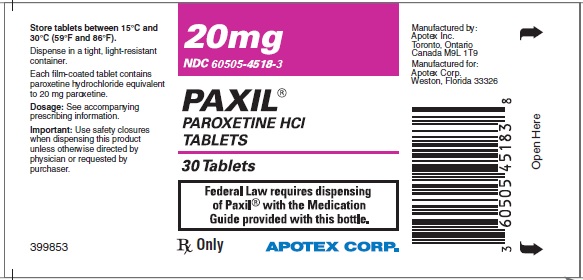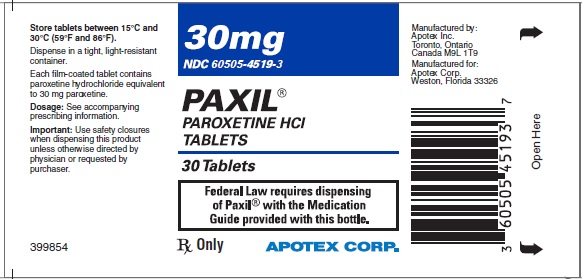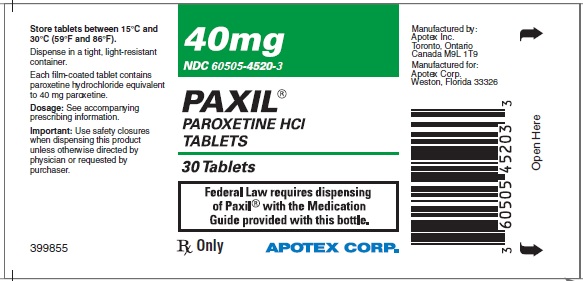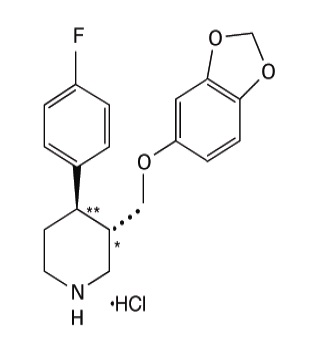 DRUG LABEL: PAXIL
NDC: 60505-4517 | Form: TABLET, FILM COATED
Manufacturer: Apotex Corp
Category: prescription | Type: HUMAN PRESCRIPTION DRUG LABEL
Date: 20241022

ACTIVE INGREDIENTS: PAROXETINE HYDROCHLORIDE 10 mg/1 1
INACTIVE INGREDIENTS: DIBASIC CALCIUM PHOSPHATE DIHYDRATE; SODIUM STARCH GLYCOLATE TYPE B POTATO; MAGNESIUM STEARATE ; HYPROMELLOSE, UNSPECIFIED; TITANIUM DIOXIDE; POLYETHYLENE GLYCOL, UNSPECIFIED; D&C YELLOW NO. 10 ; POLYSORBATE 80; FD&C YELLOW NO. 6 

HIGHLIGHTS OF PRESCRIBING INFORMATION

These highlights do not include all the information needed to use PAXIL safely and effectively. See full prescribing information for PAXIL.
PAXIL (paroxetine) tablets, for oral use
PAXIL (paroxetine) oral suspension
Initial U.S. Approval: 1992

RECENT MAJOR CHANGES

Warnings and Precautions (5.4) 11/2024

WARNING: SUICIDAL THOUGHTS AND BEHAVIORS

See full prescribing information for complete boxed warning.

Increased risk of suicidal thoughts and behavior in pediatric and young adult patients taking antidepressants. Closely monitor all antidepressant treated patients for clinical worsening and emergence of suicidal thoughts and behaviors. PAXIL is not approved for use in pediatric patients.(5.1, 8.4)

1 INDICATIONS AND USAGE

PAXIL is a selective serotonin reuptake inhibitor (SSRI) indicated in adults for the treatment of (1):

- Major Depressive Disorder (MDD)
- Obsessive Compulsive Disorder (OCD)
- Panic Disorder (PD)
- Social Anxiety Disorder (SAD)
- Generalized Anxiety Disorder (GAD)
- Posttraumatic Stress Disorder (PTSD)

2 DOSAGE AND ADMINISTRATION

- Shake oral suspension well before administration (2.1)
- Recommended starting and maximum daily dosage for MDD, OCD, PD, and PTSD: (2.2)
  Indication | Starting Daily Dose | Maximum Daily Dose
  MDD | 20 mg | 50 mg
  OCD | 20 mg | 60 mg
  PD | 10 mg | 60 mg
  PTSD | 20 mg | 50 mg
- Recommended starting dosage for SAD and GAD is 20 mg daily. (2.3)
- Elderly patients, patients with severe renal impairment or severe hepatic impairment: Starting dosage is 10 mg daily. Maximum dosage is 40 mg daily. (2.4)
- When discontinuing PAXIL, reduce dosage gradually. (2.6, 5.7)

3 DOSAGE FORMS AND STRENGTHS

- Extended-release tablets: 10 mg, scored; 20 mg, scored; 30 mg; and 40 mg tablets. (3)
- Oral suspension: 10 mg/5 mL (not currently marketed). (3)

4 CONTRAINDICATIONS

- Concomitant use of monoamine oxidase inhibitors (MAOIs) or use within 14 days of discontinuing a MAOI. (4, 5.3, 7)
- Concomitant use of pimozide or thioridazine. (4, 5.3,7)
- Known hypersensitivity to paroxetine or to any of the inactive ingredients in PAXIL. (4)

5 WARNINGS AND PRECAUTIONS

- Serotonin Syndrome: Increased risk when co-administered with other serotonergic agents, but also when taken alone. If occurs, discontinue PAXIL and serotonergic agents and initiate supportive measures. (5.2)
- Embryofetal Toxicity: May cause fetal harm. Meta-analyses of epidemiological studies have shown increased risk (less than 2-fold) of cardiovascular malformations with exposure during the first trimester. (5.4, 8.1)
- Increased Risk of Bleeding: Concomitant use of aspirin, nonsteroidal anti-inflammatory drugs, other antiplatelet drugs, warfarin, and other anticoagulant drugs may increase risk. (5.5)
- Activation of Mania/Hypomania: Screen patients for bipolar disorder. (5.6)
- Seizures: Use with caution in patients with seizure disorders. (5.8)
- Angle-Closure Glaucoma: Angle-closure glaucoma has occurred in patients with untreated anatomically narrow angles treated with antidepressants. (5.9)
- Sexual Dysfunction: PAXIL may cause symptoms of sexual dysfunction. (5.13)

6 ADVERSE REACTIONS

Most common adverse reactions (≥5% and at least twice placebo) are abnormal ejaculation, asthenia, constipation, decreased appetite, diarrhea, dizziness, dry mouth, female genital disorder, impotence, infection, insomnia, libido decreased, male genital disorder, nausea, nervousness, somnolence, sweating, tremor, yawn. (6)

To report SUSPECTED ADVERSE REACTIONS, contact Apotex Corp. at 1-800-706-5575 or FDA at 1-800-FDA-1088 or www.fda.gov/medwatch.

7 DRUG INTERACTIONS

- Drugs Highly Bound to Plasma Protein: Monitor for adverse reactions and reduce dosage of PAXIL or other protein-bound drugs (e.g., warfarin) as warranted. (7)
- Drugs Metabolized by CYP2D6: Reduce dosage of drugs metabolized by CYP2D6 as warranted. (7)
- Concomitant use with tamoxifen: Consider use of an alternative antidepressant with little or no CYP2D6 inhibition. (5.11, 7)

8 USE IN SPECIFIC POPULATIONS

- Pregnancy: SSRI use, particularly later in pregnancy, may increase the risk for persistent pulmonary hypertension and symptoms of poor adaptation (respiratory distress, temperature instability, feeding difficulty, hypotonia, irritability) in the neonate. (8.1)

FULL PRESCRIBING INFORMATION

WARNING: SUICIDAL THOUGHTS AND BEHAVIORS

Antidepressants increased the risk of suicidal thoughts and behaviors in pediatric and young adult patients in short-term studies. Closely monitor all antidepressant-treated patients for clinical worsening, and for emergence of suicidal thoughts and behaviors [see Warnings and Precautions (5.1)] . PAXIL is not approved for use in pediatric patients [see Use in Specific Populations (8.4)] .

1 INDICATIONS AND USAGE

PAXIL is indicated in adults for the treatment of:

- Major depressive disorder (MDD)
- Obsessive compulsive disorder (OCD)
- Panic disorder (PD)
- Social anxiety disorder (SAD)
- Generalized anxiety disorder (GAD)
- Posttraumatic stress disorder (PTSD)

2 DOSAGE AND ADMINISTRATION

2.1 Administration Information

Administer PAXIL as a single daily dose in the morning, with or without food.

Shake the oral suspension well before administration.

2.2 Recommended Dosage for MDD, OCD, PD, and PTSD

The recommended starting dosages and maximum dosages of PAXIL in patients with MDD, OCD, PD, and PTSD are presented in Table 1.

In patients with an inadequate response, increase dosage in increments of 10 mg per day at intervals of at least 1 week, depending on tolerability.

Table 1: Recommended Daily Dosage of PAXIL in Patients with MDD, OCD, PD, and PTSD

Indication | Starting Dose | Maximum Dose
MDD | 20 mg | 50 mg
OCD | 20 mg | 60 mg
PD | 10 mg | 60 mg
PTSD | 20 mg | 50 mg

2.3 Recommended Dosage for SAD and GAD

SAD

The starting and recommended dosage in patients with SAD is 20 mg daily. In clinical trials the effectiveness of PAXIL was demonstrated in patients dosed in a range of 20 mg to 60 mg daily. While the safety of PAXIL has been evaluated in patients with SAD at doses up to 60 mg daily, available information does not suggest any additional benefit for doses above 20 mg daily [see Clinical Studies (14.4)].

GAD

The starting and recommended dosage in patients with GAD is 20 mg daily. In clinical trials the effectiveness of PAXIL in GAD was demonstrated in patients dosed in a range of 20 mg to 50 mg daily. There is not sufficient evidence to suggest a greater benefit to doses higher than 20 mg daily [see Clinical Studies (14.5)].

In patients with an inadequate response, increase dosage in increments of 10 mg per day at intervals of at least 1 week, depending on tolerability.

2.4 Screen for Bipolar Disorder Prior to Starting PAXIL

Prior to initiating treatment with PAXIL or another antidepressant, screen patients for a personal or family history of bipolar disorder, mania, or hypomania [see Warnings and Precautions (5.6)].

2.5 Recommended Dosage for Elderly Patients, Patients with Severe Renal Impairment, and Patients with Severe Hepatic Impairment

The recommended initial dosage is 10 mg per day for elderly patients, patients with severe renal impairment, and patients with severe hepatic impairment. Dosage should not exceed 40 mg/day.

2.6 Switching Patients to or From a Monoamine Oxidase Inhibitor (MAOI)

At least 14 days must elapse between discontinuation of a monoamine oxidase inhibitor (MAOI and initiation of PAXIL. In addition, at least 14 days must elapse after stopping PAXIL before starting an MAOI antidepressant [see Contraindications (4), Warnings and Precautions (5.2)].

2.7 Discontinuation of Treatment With PAXIL

Adverse reactions may occur upon discontinuation of PAXIL [see Warnings and Precautions (5.7)]. Gradually reduce the dosage rather than stopping PAXIL abruptly whenever possible.

3 DOSAGE FORMS AND STRENGTHS

PAXIL tablets are available as:

- 10 mg yellow, scored tablet engraved on the front with “PAXIL” and on the back with “10”.
- 20 mg pink, scored tablet engraved on the front with “PAXIL” and on the back with “20”.
- 30 mg blue tablet engraved on the front with “PAXIL” and on the back with “30”.
- 40 mg green tablet engraved on the front with “PAXIL” and on the back with “40”.

PAXIL oral suspension is available as:

- 10 mg/5 mL orange colored, orange flavored suspension in bottles containing 250 mL (not currently marketed).

4 CONTRAINDICATIONS

PAXIL is contraindicated in patients:

- Taking, or within 14 days of stopping, MAOIs (including the MAOIs linezolid and intravenous methylene blue) because of an increased risk of serotonin syndrome [see Warnings and Precautions (5.2), Drug Interactions (7)].
- Taking thioridazine because of risk of QT prolongation [see Warnings and Precautions (5. 3), Drug Interactions (7)]
- Taking pimozide because of risk of QT prolongation [see Warnings and Precautions (5.3), Drug Interactions (7)]. With known hypersensitivity (e.g., anaphylaxis, angioedema, Stevens-Johnson syndrome) to paroxetine or any of the inactive ingredients in PAXIL [see Adverse Reactions (6.1), (6.2)].

5 WARNINGS AND PRECAUTIONS

5.1 Suicidal Thoughts and Behaviors in Adolescents and Young Adults

In pooled analyses of placebo-controlled trials of antidepressant drugs (SSRIs and other antidepressant classes) that included approximately 77,000 adult patients and 4,500 pediatric patients, the incidence of suicidal thoughts and behaviors in antidepressant-treated patients age 24 years and younger was greater than in placebo-treated patients. There was considerable variation in risk of suicidal thoughts and behaviors among drugs, but there was an increased risk identified in young patients for most drugs studied. There were differences in absolute risk of suicidal thoughts and behaviors across the different indications, with the highest incidence in patients with MDD. The drug-placebo differences in the number of cases of suicidal thoughts and behaviors per 1,000 patients treated are provided in Table 2.

Table 2: Risk Differences of the Number of Patients with Suicidal Thoughts and Behaviors in the Pooled Placebo-Controlled Trials of Antidepressants in Pediatric and Adult Patients

Age Range | Drug-Placebo Difference in Number of Patients with Suicidal Thoughts and Behaviors per 1,000 Patients Treated
 | Increases Compared to Placebo
<18 years old | 14 additional cases
18-24 years old | 5 additional cases
 | Decreases Compared to Placebo
25-64 years old | 1 fewer case
≥65 years old | 6 fewer cases

PAXIL is not approved for use in pediatric patients.

It is unknown whether the risk of suicidal thoughts and behaviors in children, adolescents, and young adults extends to longer-term use, i.e., beyond four months. However, there is substantial evidence from placebo-controlled maintenance trials in adults with MDD that antidepressants delay the recurrence of depression and that depression itself is a risk factor for suicidal thoughts and behaviors.

Monitor all antidepressant-treated patients for any indication for clinical worsening and emergence of suicidal thoughts and behaviors, especially during the initial few months of drug therapy, and at times of dosage changes. Counsel family members or caregivers of patients to monitor for changes in behavior and to alert the healthcare provider. Consider changing the therapeutic regimen, including possibly discontinuing PAXIL, in patients whose depression is persistently worse, or who are experiencing emergent suicidal thoughts or behaviors.

5.2 Serotonin Syndrome

SSRIs, including PAXIL, can precipitate serotonin syndrome, a potentially life-threatening condition. The risk is increased with concomitant use of other serotonergic drugs (including triptans, tricyclic antidepressants, fentanyl, lithium, tramadol, meperidine, methadone, tryptophan, buspirone, amphetamines and St. John’s Wort) and with drugs that impair metabolism of serotonin, i.e., MAOIs [see Contraindications (4), Drug Interactions (7.1)]. Serotonin syndrome can also occur when these drugs are used alone.

Serotonin syndrome symptoms may include mental status changes (e.g., agitation, hallucinations, delirium, and coma), autonomic instability (e.g., tachycardia, labile blood pressure, dizziness, diaphoresis, flushing, hyperthermia), neuromuscular symptoms (e.g., tremor, rigidity, myoclonus, hyperreflexia, incoordination), seizures, and/or gastrointestinal symptoms (e.g., nausea, vomiting, diarrhea).

The concomitant use of PAXIL with MAOIs is contraindicated. In addition, do not initiate PAXIL in a patient being treated with MAOIs such as linezolid or intravenous methylene blue. No reports involved the administration of methylene blue by other routes (such as oral tablets or local tissue injection) or at lower doses. If it is necessary to initiate treatment with an MAOI such as linezolid or intravenous methylene blue in a patient taking PAXIL discontinue PAXIL before initiating treatment with the MAOI [see Contraindications (4), Drug Interactions (7)].

Monitor all patients taking PAXIL for the emergence of serotonin syndrome. Discontinue treatment with PAXIL and any concomitant serotonergic agents immediately if the above symptoms occur, and initiate supportive symptomatic treatment. If concomitant use of PAXIL with other serotonergic drugs is clinically warranted, inform patients of the increased risk for serotonin syndrome and monitor for symptoms.

5.3 Drug Interactions Leading to QT Prolongation

The CYP2D6 inhibitory properties of paroxetine can elevate plasma levels of thioridazine and pimozide. Since thioridazine and pimozide given alone produce prolongation of the QTc interval and increase the risk of serious ventricular arrhythmias, the use of PAXIL is contraindicated in combination with thioridazine and pimozide [see Contraindications (4), Drug Interactions (7), Clinical Pharmacology (12.3)].

5.4 Embryofetal Toxicity

Based on meta-analyses of epidemiological studies, exposure to paroxetine in the first trimester of pregnancy is associated with a less than 2-fold increase in the rate of cardiovascular malformations among infants. For women who intend to become pregnant or who are in their first trimester of pregnancy, PAXIL, should be initiated only after consideration of the other available treatment options [see Use in Specific Populations (8.1)].

5.5 Increased Risk of Bleeding

Drugs that interfere with serotonin reuptake inhibition, including PAXIL, increase the risk of bleeding events. Concomitant use of aspirin, nonsteroidal anti-inflammatory drugs (NSAIDS), other antiplatelet drugs, warfarin, and other anticoagulants may add to this risk. Case reports and epidemiological studies (case-control and cohort design) have demonstrated an association between use of drugs that interfere with serotonin reuptake and the occurrence of gastrointestinal bleeding. Based on data from the published observational studies, exposure to SSRIs, particularly in the month before delivery, has been associated with a less than 2-fold increase in the risk of postpartum hemorrhage [see Use in Specific Populations (8.1)]. Bleeding events related to drugs that interfere with serotonin reuptake have ranged from ecchymoses, hematomas, epistaxis, and petechiae to life-threatening hemorrhages.

Inform patients about the increased risk of bleeding associated with the concomitant use of PAXIL and antiplatelet agents or anticoagulants. For patients taking warfarin, carefully monitor the international normalized ratio.

5.6 Activation of Mania or Hypomania

In patients with bipolar disorder, treating a depressive episode with PAXIL or another antidepressant may precipitate a mixed/manic episode. During controlled clinical trials of PAXIL, hypomania or mania occurred in approximately 1% of PAXIL-treated unipolar patients compared to 1.1% of active-control and 0.3% of placebo-treated unipolar patients. Prior to initiating treatment with PAXIL, screen patients for any personal or family history of bipolar disorder, mania, or hypomania.

5.7 Discontinuation Syndrome

Adverse reactions after discontinuation of serotonergic antidepressants, particularly after abrupt discontinuation, include: nausea, sweating, dysphoric mood, irritability, agitation, dizziness, sensory disturbances (e.g., paresthesia, such as electric shock sensations), tremor, anxiety, confusion, headache, lethargy, emotional lability, insomnia, hypomania, tinnitus, and seizures. A gradual reduction in dosage rather than abrupt cessation is recommended whenever possible [see Dosage and Administration (2.7)].

During clinical trials of GAD and PTSD, gradual decreases in the daily dose by 10 mg/day at weekly intervals followed by 1 week at 20 mg/day was used before treatment was discontinued. The following adverse reactions were reported at an incidence of 2% or greater for PAXIL and were at least twice that reported for placebo: Abnormal dreams, paresthesia, and dizziness adverse reactions have been reported upon discontinuation of treatment with PAXIL in pediatric patients. The safety and effectiveness of PAXIL in pediatric patients have not been established [see Boxed Warning, Warnings and Precautions (5.1), Use in Specific Populations (8.4)].

5.8 Seizures

PAXIL tablets and oral suspension have not been systematically evaluated in patients with seizure disorders. Patients with history of seizures were excluded from clinical studies. During clinical studies, seizures occurred in 0.1% of patients treated with PAXIL. PAXIL should be prescribed with caution in patients with a seizure disorder. Discontinue PAXIL in any patient who develops seizures.

5.9 Angle-Closure Glaucoma

The pupillary dilation that occurs following use of many antidepressant drugs including PAXIL may trigger an angle closure attack in a patient with anatomically narrow angles who does not have a patent iridectomy. Cases of angle-closure glaucoma associated with use of PAXIL have been reported. Avoid use of antidepressants, including PAXIL in patients with untreated anatomically narrow angles.

5.10 Hyponatremia

Hyponatremia may occur as a result of treatment with SSRIs, including PAXIL. Cases with serum sodium lower than 110 mmol/L have been reported. Signs and symptoms of hyponatremia include headache, difficulty concentrating, memory impairment, confusion, weakness, and unsteadiness, which may lead to falls. Signs and symptoms associated with more severe and/or acute cases have included hallucination, syncope, seizure, coma, respiratory arrest, and death. In many cases, this hyponatremia appears to be the result of the syndrome of inappropriate antidiuretic hormone secretion (SIADH).

In patients with symptomatic hyponatremia, discontinue PAXIL and institute appropriate medical intervention. Elderly patients, patients taking diuretics, and those who are volume-depleted may be at greater risk of developing hyponatremia with SSRIs [see Use in Specific Populations (8.5)].

5.11 Reduction of Efficacy of Tamoxifen

Some studies have shown that the efficacy of tamoxifen, as measured by the risk of breast cancer relapse/mortality, may be reduced with concomitant use of PAXIL as a result of paroxetine’s irreversible inhibition of CYP2D6 and lower blood levels of tamoxifen [see Drug Interactions (7)]. One study suggests that the risk may increase with longer duration of coadministration. However, other studies have failed to demonstrate such a risk. When tamoxifen is used for the treatment or prevention of breast cancer, prescribers should consider using an alternative antidepressant with little or no CYP2D6 inhibition.

5.12 Bone Fracture

Epidemiological studies on bone fracture risk during exposure to some antidepressants, including SSRIs, have reported an association between antidepressant treatment and fractures. There are multiple possible causes for this observation, and it is unknown to what extent fracture risk is directly attributable to SSRI treatment.

5.13 Sexual Dysfunction

Use of SSRIs, including PAXIL, may cause symptoms of sexual dysfunction [see Adverse Reactions (6.1)]. In male patients, SSRI use may result in ejaculatory delay or failure, decreased libido, and erectile dysfunction. In female patients, SSRI use may result in decreased libido and delayed or absent orgasm.

It is important for prescribers to inquire about sexual function prior to initiation of PAXIL and to inquire specifically about changes in sexual function during treatment, because sexual function may not be spontaneously reported. When evaluating changes in sexual function, obtaining a detailed history (including timing of symptom onset) is important because sexual symptoms may have other causes, including the underlying psychiatric disorder. Discuss potential management strategies to support patients in making informed decisions about treatment.

6 ADVERSE REACTIONS

The following adverse reactions are included in more detail in other sections of the prescribing information:

- Hypersensitivity reactions to paroxetine [see Contraindications (4)]
- Suicidal Thoughts and Behaviors [see Warnings and Precautions (5.1)]
- Serotonin Syndrome [see Warnings and Precautions (5.2)]
- Embryofetal Toxicity [see Warnings and Precautions (5.4)]
- Increased Risk of Bleeding [see Warnings and Precautions (5.5)]
- Activation of Mania/Hypomania [see Warnings and Precautions (5.6)]
- Discontinuation Syndrome [see Warnings and Precautions (5.7)]
- Seizures [see Warnings and Precautions (5.8)]
- Angle-closure Glaucoma [see Warnings and Precautions (5.9)]
- Hyponatremia [see Warnings and Precautions (5.10)]
- Bone Fracture [see Warnings and Precautions (5.12)]
- Sexual Dysfunction [see Warnings and Precautions (5.13)]

6.1 Clinical Trials Experience

Because clinical trials are conducted under widely varying conditions, adverse reaction rates observed in the clinical trials of a drug cannot be directly compared to rates in the clinical trials of another drug and may not reflect the rates observed in practice.

The safety data for PAXIL are from:

- 6‑week clinical trials in MDD patients who received PAXIL 20 mg to 50 mg once daily
- 12-week clinical trials in OCD patients who received PAXIL 20 mg to 60 mg once daily
- 10‑ to 12‑week clinical trials in PD patients who received PAXIL 10 mg to 60 mg once daily
- 12-week clinical trials in SAD patients who received PAXIL 20 mg to 50 mg once daily
- 8‑week clinical trials in GAD patients who received PAXIL 10 mg to 50 mg once daily
- 12‑week clinical trials in PTSD patients who received PAXIL 20 mg to 50 mg once daily

Adverse Reactions Leading to Discontinuation

Twenty percent (1,199/6,145) of patients treated with PAXIL in clinical trials in MDD and 16.1% (84/522), 11.8% (64/542), 9.4% (44/469), 10.7% (79/735), and 11.7% (79/676) of patients treated with PAXIL in clinical trials in SAD, OCD, PD, GAD, and PTSD, respectively, discontinued treatment due to an adverse reaction. The most common adverse reactions (≥1%) associated with discontinuation (i.e., those adverse reactions associated with dropout at a rate approximately twice or greater for PAXIL compared to placebo) are presented in Table 3:

Table 3: Adverse Reactions Reported as Leading to Discontinuation (≥1% of PAXIL-Treated Patients and Greater than Placebo) in MDD, OCD, PD, SAD, GAD, and PTSD Trials

 | MDD |  | OCD |  | PD |  | SAD |  | GAD |  | PTSD
 | PAXIL % | Placebo % | PAXIL % | Placebo % | PAXIL % | Placebo % | PAXIL % | Placebo % | PAXIL % | Placebo % | PAXIL % | Placebo %
CNS
Somnolence | 2.3 | 0.7 | --- |  | 1.9 | 0.3 | 3.4 | 0.3 | 2.0 | 0.2 | 2.8 | 0.6
Insomnia | --- | --- | 1.7 | 0 | 1.3 | 0.3 | 3.1 | 0 |  |  | --- | ---
Agitation | 1.1 | 0.5 | --- |  |  |  |  |  |  |  | --- | ---
Tremor | 1.1 | 0.3 | --- |  |  |  | 1.7 | 0 |  |  | 1.0 | 0.2
Anxiety | --- | --- | --- |  |  |  | 1.1 | 0 |  |  | --- | ---
Dizziness | --- | --- | 1.5 | 0 |  |  | 1.9 | 0 | 1.0 | 0.2 | --- | ---
Gastrointestinal
Constipation | --- |  | 1.1 | 0 |  |  |  |  |  |  | --- | ---
Nausea | 3.2 | 1.1 | 1.9 | 0 | 3.2 | 1.2 | 4.0 | 0.3 | 2.0 | 0.2 | 2.2 | 0.6
Diarrhea | 1.0 | 0.3 | ---
Dry mouth | 1.0 | 0.3 | --- |  |  |  |  |  |  |  | --- | ---
Vomiting | 1.0 | 0.3 | --- |  |  |  | 1.0 | 0 |  |  | --- | ---
Flatulence |  |  |  |  |  |  | 1.0 | 0.3 |  |  | --- | ---
Other
Asthenia | 1.6 | 0.4 | 1.9 | 0.4 |  |  | 2.5 | 0.6 | 1.8 | 0.2 | 1.6 | 0.2
Abnormal Ejaculationa | 1.6 | 0 | 2.1 | 0 |  |  | 4.9 | 0.6 | 2.5 | 0.5 | --- | ---
Sweating | 1.0 | 0.3 | --- |  |  |  | 1.1 | 0 | 1.1 | 0.2 | --- | ---
Impotencea | --- |  | 1.5 | 0 |  |  |  |  |  |  | --- | ---
Libido Decreased |  |  |  |  |  |  | 1.0 | 0 |  |  | --- | ---

Where numbers are not provided the incidence of the adverse reactions in patients treated with PAXIL was not >1% or was not greater than or equal to 2 times the incidence of placebo. a. Incidence corrected for gender.

Most Common Adverse Reactions

The most commonly observed adverse reactions associated with the use of PAXIL (incidence of 5% or greater and at least twice that for placebo) were:

MDD: Asthenia, sweating, nausea, decreased appetite, somnolence, dizziness, insomnia, tremor, nervousness, ejaculatory disturbance, and other male genital disorders.

OCD: Nausea, dry mouth, decreased appetite, constipation, dizziness, somnolence, tremor, sweating, impotence, and abnormal ejaculation.

PD: Asthenia, sweating, decreased appetite, libido decreased, tremor, abnormal ejaculation, female genital disorders, and impotence.

SAD: Sweating, nausea, dry mouth, constipation, decreased appetite, somnolence, tremor, libido decreased, yawn, abnormal ejaculation, female genital disorders, and impotence.

GAD: Asthenia, infection, constipation, decreased appetite, dry mouth, nausea, libido decreased, somnolence, tremor, sweating, and abnormal ejaculation.

PTSD: Asthenia, sweating, nausea, dry mouth, diarrhea, decreased appetite, somnolence, libido decreased, abnormal ejaculation, female genital disorders, and impotence.

Adverse Reactions in Patients with MDD

Table 4 presents the adverse reactions that occurred at an incidence of 1% or more and greater than placebo in clinical trials of PAXIL‑treated patients with MDD.

Table 4: Adverse Reactions (≥1% of PAXIL-Treated Patients and Greater than Placebo) in 6-Week Clinical Trials for MDD

Body System/ Adverse Reaction | PAXIL (n = 421) % | Placebo (n = 421) %
Body as a Whole
Headache | 18 | 17
Asthenia | 15 | 6
Cardiovascular
Palpitation | 3 | 1
Vasodilation | 3 | 1
Dermatologic
Sweating | 11 | 2
Rash | 2 | 1
Gastrointestinal
Nausea | 26 | 9
Dry Mouth | 18 | 12
Constipation | 14 | 9
Diarrhea | 12 | 8
Decreased Appetite | 6 | 2
Flatulence | 4 | 2
Oropharynx Disordera | 2 | 0
Dyspepsia | 2 | 1
Musculoskeletal
Myopathy | 2 | 1
Myalgia | 2 | 1
Myasthenia | 1 | 0
Nervous System
Somnolence | 23 | 9
Dizziness | 13 | 6
Insomnia | 13 | 6
Tremor | 8 | 2
Nervousness | 5 | 3
Anxiety | 5 | 3
Paresthenia | 4 | 2
Libido Decreased | 3 | 0
Drugged Feeling | 2 | 1
Confusion | 1 | 0
Respiration
Yawn | 4 | 0
Special Senses
Blurred Vision | 4 | 1
Taste Perversion | 2 | 0
Urogential System
Ejaculatory Disturbanceb,c | 13 | 0
Other Male Genital Disordersb,d | 10 | 0
Urinary Frequency | 3 | 1
Urination Disordere | 3 | 0
Female Genital Disordersb,f | 2 | 0

a. Includes mostly “lump in throat” and “tightness in throat.”

b. Percentage corrected for gender.

c. Mostly “ejaculatory delay.”

d. Includes “anorgasmia,” “erectile difficulties,” “delayed ejaculation/orgasm,” and “sexual dysfunction,” and “impotence.”

e. Includes mostly “difficulty with micturition” and “urinary hesitancy.”

f. Includes mostly “anorgasmia” and “difficulty reaching climax/orgasm.”

Adverse Reactions in Patients with OCD, PD, and SAD

Table 5 presents adverse reactions that occurred at a frequency of 2% or more in clinical trials in patients with OCD, PD, and SAD.

Table 5. Adverse Reactions (≥2% of PAXIL-Treated Patients and Greater than Placebo) in 10 to 12-Week Clinical Trials for OCD, PD, and SAD

Body System/Preferred Term | Obsessive Compulsive Disorder |  | Panic Disorder |  | Social Anxiety Disorder
Body System/Preferred Term | PAXIL (n = 542) % | Placebo (n = 265) % | PAXIL (n = 469) % | Placebo (n = 425) % | PAXIL (n = 425) % | Placebo (n = 339) %
Body as a Whole
Asthenia | 22 | 14 | 14 | 5 | 22 | 14
Abdominal Pain | --- | --- | 4 | 3 | --- | ---
Chest Pain | 3 | 2 | --- | --- | --- | ---
Back Pain | --- | --- | 3 | 2 | --- | ---
Chills | 2 | 1 | 2 | 1 | --- | ---
Trauma | --- | --- | --- | --- | 3 | 1
Cardiovascular
Vasodilation | 4 | 1 | --- | --- | --- | ---
Palpitation | 2 | 0 | --- | --- | --- | ---
Dermatologic
Sweating | 9 | 3 | 14 | 6 | 9 | 2
Rash | 3 | 2 | --- | --- | --- | ---
Gastrointestinal
Nausea | 23 | 10 | 23 | 17 | 25 | 7
Dry Mouth | 18 | 9 | 18 | 11 | 9 | 3
Constipation | 16 | 6 | 8 | 5 | 5 | 2
Diarrhea | 10 | 10 | 12 | 7 | 9 | 6
Decreased Appetite | 9 | 3 | 7 | 3 | 8 | 2
Dyspepsia | --- | --- | --- | --- | 4 | 2
Flatulence | --- | --- | --- | --- | 4 | 2
Increased Appetite | 4 | 3 | 2 | 1 | --- | ---
Vomiting | --- | --- | --- | --- | 2 | 1
Musculoskeletal
Myalgia | --- | --- | --- | --- | 4 | 3
Nervous System
Insomnia | 24 | 13 | 18 | 10 | 21 | 16
Somnolence | 24 | 7 | 19 | 11 | 22 | 5
Dizziness | 12 | 6 | 14 | 10 | 11 | 7
Tremor | 11 | 1 | 9 | 1 | 9 | 1
Nervousness | 9 | 8 | --- | --- | 8 | 7
Libido Decreased | 7 | 4 | 9 | 1 | 12 | 1
Agitation | --- | --- | 5 | 4 | 3 | 1
Anxiety | --- | --- | 5 | 4 | 5 | 4
Abnormal Dreams | 4 | 1 | --- | --- | --- | ---
Concentration Impaired | 3 | 2 | --- | --- | 4 | 1
Depersonalization | 3 | 0 | --- | --- | --- | ---
Myoclonus | 3 | 0 | 3 | 2 | 2 | 1
Amnesia | 2 | 1 | --- | --- | --- | ---
Respiratory System
Rhinitis | --- | --- | 3 | 0 | --- | ---
Pharyngitis | --- | --- | --- | --- | 4 | 2
Yawn | --- | --- | --- | --- | 5 | 1
Special Senses
Abnormal Vision | 4 | 2 | --- | --- | 4 | 1
Taste Perversion | 2 | 0 | --- | --- | --- | ---
Urogenital System
Abnormal Ejaculationa | 23 | 1 | 21 | 1 | 28 | 1
Dysmenorrhea | --- | --- | --- | --- | 5 | 4
Female Genital Disordera | 3 | 0 | 9 | 1 | 9 | 1
Impotencea | 8 | 1 | 5 | 0 | 5 | 1
Urinary Frequency | 3 | 1 | 2 | 0 | --- | ---
Urination Impaired | 3 | 0 | --- | --- | --- | ---
Urinary Tract Infection | 2 | 1 | 2 | 1 | --- | ---

a. Percentage corrected for gender.

Adverse Reactions in Patients with GAD and PTSD

Table 6 presents adverse reactions that occurred at a frequency of 2% or more in clinical trials in patients with GAD and PTSD.

Table 6. Adverse Reactions (≥2% of PAXIL-Treated Patients and Greater than Placebo) in 8- to 12-Week Clinical Trials for GAD and PTSDa

Body System/Preferred Term | Generalized Anxiety Disorder |  | Posttraumatic Stress Disorder
Body System/Preferred Term | PAXIL (n = 735) % | Placebo (n = 529) % | PAXIL (n = 576) % | Placebo (n = 504) %
Body as a Whole
Asthenia | 14 | 6 | 12 | 4
Headache | 17 | 14 | --- | ---
Infection | 6 | 3 | 5 | 4
Abdominal Pain |  |  | 4 | 3
Trauma |  |  | 6 | 5
Cardiovascular
Vasodilation | 3 | 1 | 2 | 1
Dermatologic
Sweating | 6 | 2 | 5 | 1
Gastrointestinal
Nausea | 20 | 5 | 19 | 8
Dry Mouth | 11 | 5 | 10 | 5
Constipation | 10 | 2 | 5 | 3
Diarrhea | 9 | 7 | 11 | 5
Decreased Appetite | 5 | 1 | 6 | 3
Vomiting | 3 | 2 | 3 | 2
Dyspepsia | --- | --- | 5 | 3
Nervous System
Insomnia | 11 | 8 | 12 | 11
Somnolence | 15 | 5 | 16 | 5
Dizziness | 6 | 5 | 6 | 5
Tremor | 5 | 1 | 4 | 1
Nervousness | 4 | 3 | --- | ---
Libido Decreased | 9 | 2 | 5 | 2
Abnormal Dreams |  |  | 3
Respiratory System
Respiratory Disorder | 7 | 5 | --- | ---
Sinusitis | 4 | 3 | --- | ---
Yawn | 4 | --- | 2 | <1
Special Senses
Abnormal Vision | 2 | 1 | 3 | 1
Urogenital System
Abnormal Ejaculationa | 25 | 2 | 13 | 2
Female Genital Disordera | 4 | 1 | 5 | 1
Impotencea | 4 | 3 | 9 | 1

a. Percentage corrected for gender.

Dose Dependent Adverse Reactions

MDD

A comparison of adverse reaction rates in a fixed‑dose study comparing PAXIL10 mg, 20 mg, 30 mg, and 40 mg once daily with placebo in the treatment of MDD revealed dose dependent adverse reactions, as shown in Table 7:

Table 7. Adverse Reactions (≥5% of PAXIL-Treated Patients and ≥ Twice the Rate of Placebo) (in a Dose‑Comparison Trial in the Treatment of MDD

Body System/Preferred Term | Placebo | PAXIL
Body System/Preferred Term | n = 51 % | 10 mg n = 102 % | 20 mg n = 104 % | 30 mg n = 101 % | 40 mg n = 104 %
Body as a Whole
Asthenia | 0.0 | 2.9 | 10.6 | 13.9 | 12.7
Dermatology
Sweating | 2.0 | 1.0 | 6.7 | 8.9 | 11.8
Gastrointestinal
Constipation | 5.9 | 4.9 | 7.7 | 9.9 | 12.7
Decreased Appetite | 2.0 | 2.0 | 5.8 | 4.0 | 4.9
Diarrhea | 7.8 | 9.8 | 19.2 | 7.9 | 14.7
Dry Mouth | 2.0 | 10.8 | 18.3 | 15.8 | 20.6
Nausea | 13.7 | 14.7 | 26.9 | 34.7 | 36.3
Nervous System
Anxiety | 0.0 | 2.0 | 5.8 | 5.9 | 5.9
Dizziness | 3.9 | 6.9 | 6.7 | 8.9 | 12.7
Nervousness | 0.0 | 5.9 | 5.8 | 4.0 | 2.9
Paresthesia | 0.0 | 2.9 | 1.0 | 5.0 | 5.9
Somnolence | 7.8 | 12.7 | 18.3 | 20.8 | 21.6
Tremor | 0.0 | 0.0 | 7.7 | 7.9 | 14.7
Special Senses
Blurred Vision | 2.0 | 2.9 | 2.9 | 2.0 | 7.8
Urogenital System
Abnormal Ejaculation | 0.0 | 5.8 | 6.5 | 10.6 | 13.0
Impotence | 0.0 | 1.9 | 4.3 | 6.4 | 1.9
Male Genital Disorders | 0.0 | 3.8 | 8.7 | 6.4 | 3.7

OCD

In a fixed‑dose study comparing placebo and PAXIL 20 mg, 40 mg, and 60 mg in the treatment of OCD, there was no clear relationship between adverse reactions and the dose of PAXIL to which patients were assigned.

PD

In a fixed-dose study comparing placebo and PAXIL 10 mg, 20 mg, and 40 mg in the treatment of PD, the following adverse reactions were shown to be dose-dependent: asthenia, dry mouth, anxiety, libido decreased, tremor, and abnormal ejaculation.

SAD

In a fixed‑dose study comparing placebo and PAXIL 20 mg, 40 mg and 60 mg in the treatment of SAD, for most of the adverse reactions, there was no clear relationship between adverse reactions and the dose of PAXIL to which patients were assigned.

GAD

In a fixed‑dose study comparing placebo and PAXIL 20 mg and 40 mg in the treatment of GAD, the following adverse reactions were shown to be dose-dependent: asthenia, constipation, and abnormal ejaculation.

PTSD

In a fixed‑dose study comparing placebo and PAXIL 20 mg and 40 mg in the treatment of PTSD, the following adverse reactions were shown to be dose-dependent: impotence and abnormal ejaculation.

Male and Female Sexual Dysfunction

Although changes in sexual desire, sexual performance, and sexual satisfaction often occur as manifestations of a psychiatric disorder, they may also be a consequence of SSRI treatment. However, reliable estimates of the incidence and severity of untoward experiences involving sexual desire, performance, and satisfaction are difficult to obtain, however, in part because patients and healthcare providers may be reluctant to discuss them. Accordingly, estimates of the incidence of untoward sexual experience and performance cited in labeling may underestimate their actual incidence.

The percentage of patients reporting symptoms of sexual dysfunction in males and females with MDD, OCD, PD, SAD, GAD, and PTSD are displayed in Table 8.

Table 8. Adverse Reactions Related to Sexual Dysfunction in Patients Treated with PAXIL in Clinical Trials of MDD, OCD, PD, SAD, GAD, and PTSD

 | PAXIL | Placebo
n (males) | 1446 % | 1042 %
Decreased Libido | 6 to 15 | 0 to 5
Ejaculatory Disturbance | 13 to 28 | 0 to 2
Impotence | 2 to 9 | 0 to 3
n (females) | 1822 % | 1340 %
Decreased Libido | 0 to 9 | 0 to 2
Orgasmic Disturbance | 2 to 9 | 0 to 1

PAXIL treatment has been associated with several cases of priapism. In those cases with a known outcome, patients recovered without sequelae.

Hallucinations

In pooled clinical trials of PAXIL, hallucinations were observed in 0.2% of PAXIL-treated patients compared to 0.1% of patients receiving placebo.

Less Common Adverse Reactions

The following adverse reactions occurred during the clinical studies of PAXIL and are not included elsewhere in the labeling. Adverse reactions are categorized by body system and listed in order of decreasing frequency according to the following definitions: Frequent adverse reactions are those occurring on 1 or more occasions in at least 1/100 patients; infrequent adverse reactions are those occurring in 1/100 to 1/1,000 patients; rare adverse reactions are those occurring in fewer than 1/1,000 patients.

Body as a Whole

Infrequent: Allergic reaction, chills, face edema, malaise, neck pain; rare: Adrenergic syndrome, cellulitis, moniliasis, neck rigidity, pelvic pain, peritonitis, sepsis, ulcer.

Cardiovascular System

Frequent: Hypertension, tachycardia; infrequent: Bradycardia, hematoma, hypotension, migraine, postural hypotension, syncope; rare: Angina pectoris, arrhythmia nodal, atrial fibrillation, bundle branch block, cerebral ischemia, cerebrovascular accident, congestive heart failure, heart block, low cardiac output, myocardial infarct, myocardial ischemia, pallor, phlebitis, pulmonary embolus, supraventricular extrasystoles, thrombophlebitis, thrombosis, varicose vein, vascular headache, ventricular extrasystoles.

Digestive System

Infrequent: Bruxism, colitis, dysphagia, eructation, gastritis, gastroenteritis, gingivitis, glossitis, increased salivation, abnormal liver function tests, rectal hemorrhage, ulcerative stomatitis; rare: Aphthous stomatitis, bloody diarrhea, bulimia, cardiospasm, cholelithiasis, duodenitis, enteritis, esophagitis, fecal impactions, fecal incontinence, gum hemorrhage, hematemesis, hepatitis, ileitis, ileus, intestinal obstruction, jaundice, melena, mouth ulceration, peptic ulcer, salivary gland enlargement, sialadenitis, stomach ulcer, stomatitis, tongue discoloration, tongue edema, tooth caries.

Endocrine System

Rare: Diabetes mellitus, goiter, hyperthyroidism, hypothyroidism, thyroiditis.

Hemic and Lymphatic Systems

Infrequent: Anemia, leukopenia, lymphadenopathy, purpura; rare: Abnormal erythrocytes, basophilia, bleeding time increased, eosinophilia, hypochromic anemia, iron deficiency anemia, leukocytosis, lymphedema, abnormal lymphocytes, lymphocytosis, microcytic anemia, monocytosis, normocytic anemia, thrombocythemia, thrombocytopenia.

Metabolic and Nutritional

Frequent: Weight gain; infrequent: Edema, peripheral edema, SGOT increased, SGPT increased, thirst, weight loss; rare: Alkaline phosphatase increased, bilirubinemia, BUN increased, creatinine phosphokinase increased, dehydration, gamma globulins increased, gout, hypercalcemia, hypercholesteremia, hyperglycemia, hyperkalemia, hyperphosphatemia, hypocalcemia, hypoglycemia, hypokalemia, hyponatremia, ketosis, lactic dehydrogenase increased, non‑protein nitrogen (NPN) increased.

Musculoskeletal System

Frequent: Arthralgia; infrequent: Arthritis, arthrosis; rare: Bursitis, myositis, osteoporosis, generalized spasm, tenosynovitis, tetany.

Nervous System

Frequent: Emotional lability, vertigo; infrequent: Abnormal thinking, alcohol abuse, ataxia, dystonia, dyskinesia, euphoria, hostility, hypertonia, hypesthesia, hypokinesia, incoordination, lack of emotion, libido increased, manic reaction, neurosis, paralysis, paranoid reaction; rare: Abnormal gait, akinesia, antisocial reaction, aphasia, choreoathetosis, circumoral paresthesias, convulsion, delirium, delusions, diplopia, drug dependence, dysarthria, extrapyramidal syndrome, fasciculations, grand mal convulsion, hyperalgesia, hysteria, manic-depressive reaction, meningitis, myelitis, neuralgia, neuropathy, nystagmus, peripheral neuritis, psychotic depression, psychosis, reflexes decreased, reflexes increased, stupor, torticollis, trismus, withdrawal syndrome.

Respiratory System

Infrequent: Asthma, bronchitis, dyspnea, epistaxis, hyperventilation, pneumonia, respiratory flu; rare: Emphysema, hemoptysis, hiccups, lung fibrosis, pulmonary edema, sputum increased, stridor, voice alteration.

Skin and Appendages

Frequent: Pruritus; infrequent: Acne, alopecia, contact dermatitis, dry skin, ecchymosis, eczema, herpes simplex, photosensitivity, urticaria; rare: Angioedema, erythema nodosum, erythema multiforme, exfoliative dermatitis, fungal dermatitis, furunculosis; herpes zoster, hirsutism, maculopapular rash, seborrhea, skin discoloration, skin hypertrophy, skin ulcer, sweating decreased, vesiculobullous rash.

Special Senses

Frequent: Tinnitus; infrequent: Abnormality of accommodation, conjunctivitis, ear pain, eye pain, keratoconjunctivitis, mydriasis, otitis media; rare: Amblyopia, anisocoria, blepharitis, cataract, conjunctival edema, corneal ulcer, deafness, exophthalmos, eye hemorrhage, glaucoma, hyperacusis, night blindness, otitis externa, parosmia, photophobia, ptosis, retinal hemorrhage, taste loss, visual field defect.

Urogenital System

Infrequent: Amenorrhea, breast pain, cystitis, dysuria, hematuria, menorrhagia, nocturia, polyuria, pyuria, urinary incontinence, urinary retention, urinary urgency, vaginitis; rare: Abortion, breast atrophy, breast enlargement, endometrial disorder, epididymitis, female lactation, fibrocystic breast, kidney calculus, kidney pain, leukorrhea, mastitis, metrorrhagia, nephritis, oliguria, salpingitis, urethritis, urinary casts, uterine spasm, urolith, vaginal hemorrhage, vaginal moniliasis.

6.2 Postmarketing Experience

The following reactions have been identified during post approval use of PAXIL. Because these reactions are reported voluntarily from a population of unknown size, it is not always possible to reliably estimate their frequency or establish a causal relationship to drug exposure.

Acute pancreatitis, elevated liver function tests (the most severe cases were deaths due to liver necrosis, and grossly elevated transaminases associated with severe liver dysfunction), Guillain‑Barré syndrome, Stevens-Johnson syndrome, toxic epidermal necrolysis, drug reaction with eosinophilia and systemic symptoms (DRESS), syndrome of inappropriate ADH secretion, prolactinemia and galactorrhea; extrapyramidal symptoms which have included akathisia, bradykinesia, cogwheel rigidity, oculogyric crisis which has been associated with concomitant use of pimozide; status epilepticus, acute renal failure, pulmonary hypertension, allergic alveolitis, anosmia, hyposmia, anaphylaxis, eclampsia, laryngismus, optic neuritis, porphyria, restless legs syndrome (RLS), ventricular fibrillation, ventricular tachycardia (including torsade de pointes), hemolytic anemia, events related to impaired hematopoiesis (including aplastic anemia, pancytopenia, bone marrow aplasia, and agranulocytosis), vasculitic syndromes (such as Henoch-Schönlein purpura), and premature births in pregnant women. There has been a case report of severe hypotension when PAXIL was added to chronic metoprolol treatment.

7 DRUG INTERACTIONS

Table 9 presents clinically significant drug interactions with PAXIL.

Table 9 : Clinically Significant Drug Interactions with PAXIL

Monoamine Oxidase Inhibitors (MAOIs)
Clinical Impact | The concomitant use of SSRIs, including PAXIL, and MAOIs increases the risk of serotonin syndrome.
Intervention | PAXIL is contraindicated in patients taking MAOIs, including MAOIs such as linezolid or intravenous methylene blue [see Dosage and Administration (2.5), Contraindications (4), Warnings and Precautions (5.2)].
Examples | selegiline, tranylcypromine, isocarboxazid, phenelzine, linezolid, methylene blue
Pimozide and Thioridazine
Clinical Impact | Increased plasma concentrations of pimozide and thioridazine, drugs with a narrow therapeutic index, may increase the risk of QTc prolongation and ventricular arrhythmias.
Intervention | PAXIL is contraindicated in patients taking pimozide or thioridazine [see Contraindications (4)].
Other Serotonergic Drugs
Clinical Impact | The concomitant use of serotonergic drugs with PAXIL increases the risk of serotonin syndrome.
Intervention | Monitor patients for signs and symptoms of serotonin syndrome, particularly during treatment initiation and dosage increases. If serotonin syndrome occurs, consider discontinuation of PAXIL and/or concomitant serotonergic drugs [see Warnings and Precautions (5.2)].
Examples | other SSRIs, SNRIs, triptans, tricyclic antidepressants, opioids, lithium, tryptophan, buspirone, amphetamines, and St. John’s Wort.
Drugs that Interfere with Hemostasis (antiplatelet agents and anticoagulants)
Clinical Impact | The concurrent use of an antiplatelet agent or anticoagulant with PAXIL may potentiate the risk of bleeding.
Intervention | Inform patients of the increased risk of bleeding associated with the concomitant use of PAXIL and antiplatelet agents and anticoagulants. For patients taking warfarin, carefully monitor the international normalized ratio [see Warnings and Precautions (5.5)].
Examples | aspirin, clopidogrel, heparin, warfarin
Drugs Highly Bound to Plasma Protein
Clinical Impact | PAXIL is highly bound to plasma protein. The concomitant use of PAXIL with another drug that is highly bound to plasma protein may increase free concentrations of PAXIL or other tightly-bound drugs in plasma.
Intervention | Monitor for adverse reactions and reduce dosage of PAXIL or other protein-bound drugs as warranted.
Examples | warfarin
Drugs Metabolized by CYP2D6
Clinical Impact | PAXIL is a CYP2D6 inhibitor [see Clinical Pharmacology (12.3)]. The concomitant use of PAXIL with a CYP2D6 substrate may increase the exposure of the CYP2D6 substrate.
Intervention | Decrease the dosage of a CYP2D6 substrate if needed with concomitant PAXIL use. Conversely, an increase in dosage of a CYP2D6 substrate may be needed if PAXIL is discontinued.
Examples | propafenone, flecainide, atomoxetine, desipramine, dextromethorphan, metoprolol, nebivolol, perphenazine, tolterodine, venlafaxine, risperidone.
Tamoxifen
Clinical Impact | Concomitant use of tamoxifen with PAXIL may lead to reduced plasma concentrations of the active metabolite (endoxifen) and reduced efficacy of tamoxifen
Intervention | Consider use of an alternative antidepressant with little or no CYP2D6 inhibition [see Warnings and Precautions (5.11)].
Fosamprenavir/Ritonavir
Clinical Impact | Co-administration of fosamprenavir/ritonavir with PAXIL significantly decreased plasma levels of PAXIL.
Intervention | Any dose adjustment should be guided by clinical effect (tolerability and efficacy).

8 USE IN SPECIFIC POPULATIONS

8.1 Pregnancy

Pregnancy Exposure Registry

There is a pregnancy exposure registry that monitors pregnancy outcomes in women exposed to antidepressants, including PAXIL, during pregnancy. Healthcare providers are encouraged to advise patients to register by calling the National Pregnancy Registry for Antidepressants 1-866-961-2388 or visiting online at https://womensmentalhealth.org/clinical-and-research-programs/pregnancyregistry/antidepressants/.

Risk Summary

Based on data from published observational studies, exposure to SSRIs, particularly in the month before delivery, has been associated with a less than 2-fold increase in the risk of postpartum hemorrhage [see Warnings and Precautions (5.5) and Clinical Considerations].

Paxil is associated with a less than 2-fold increase in cardiovascular malformations when administered to a pregnant woman during the first trimester. While individual epidemiological studies on the association between paroxetine use and cardiac malformations have reported inconsistent findings, some meta-analyses of epidemiological studies have identified an increased risk of cardiovascular malformations (see Data). There are risks of persistent pulmonary hypertension of the newborn (PPHN) (see Data) and/or poor neonatal adaptation with exposure to selective serotonin reuptake inhibitors (SSRIs), including PAXIL during pregnancy. There also are risks associated with untreated depression in pregnancy (see Clinical Considerations). For women who intend to become pregnant or who are in their first trimester of pregnancy, paroxetine should be initiated only after consideration of the other available treatment options.

No evidence of treatment related malformations was observed in animal reproduction studies, when paroxetine was administered during the period of organogenesis at doses up to 50 mg/kg/day in rats and 6 mg/kg/day in rabbits. These doses are approximately 8 (rat) and less than 2 (rabbit) times the maximum recommended human dose (MRHD – 60 mg) on an mg/m2 basis. When paroxetine was administered to female rats during the last trimester of gestation and continued through lactation, there was an increase in the number of pup deaths during the first four days of lactation. This effect occurred at a dose of 1 mg/kg/day which is less than the MRHD on an mg/m2 basis (See Data).

The background risks of major birth defects and miscarriage for the indicated populations are unknown. All pregnancies have a background risk of birth defect, loss, or other adverse outcomes. In the US general population, the estimated background risk of major birth defects and miscarriage in clinically recognized pregnancies is 2 to 4% and 15 to 20%, respectively.

Clinical Considerations

Disease-associated maternal and/or embryofetal risk

Women who discontinue antidepressants during pregnancy are more likely to experience a relapse of major depression than women who continue antidepressants. This finding is from a prospective, longitudinal study of 201 pregnant women with a history of major depressive disorder who were euthymic and taking antidepressants at the beginning of pregnancy. Consider the risk of untreated depression when discontinuing or changing treatment with antidepressant medication during pregnancy and the postpartum.

Maternal Adverse Reactions

Use of PAXIL in the month before delivery may be associated with an increased risk of postpartum hemorrhage [see Warnings and Precautions (5.5)].

Fetal/Neonatal adverse reactions

Neonates exposed to PAXIL and other SSRIs late in the third trimester have developed complications requiring prolonged hospitalization, respiratory support, and tube feeding. Such complications can arise immediately upon delivery. Reported clinical findings have included respiratory distress, cyanosis, apnea, seizures, temperature instability, feeding difficulty, vomiting, hypoglycemia, hypotonia, hypertonia, hyperreflexia, tremors, jitteriness, irritability, and constant crying. These findings are consistent with either a direct toxic effect of SSRIs or possibly a drug discontinuation syndrome. It should be noted that, in some cases, the clinical picture is consistent with serotonin syndrome [see Warnings and Precautions (5.4)].

Data

Human Data

Published epidemiological studies on the association between first trimester paroxetine use and cardiovascular malformations have reported inconsistent results; however, meta-analyses of population-based cohort studies published between 1996 – 2017 indicate a less than 2-fold increased risk for overall cardiovascular malformations. Specific cardiac malformations identified in two meta-analyses include an approximately 2 to 2.5-fold increased risk for right ventricular outflow tract defects. One meta-analysis also identified an increased risk (less than 2-fold) for bulbus cordis anomalies and anomalies of cardiac septal closure, and an increased risk for atrial septal defect (pooled OR 2.38, 95% CI 1.14-4.97). Important limitations of the studies included in these meta-analyses include potential confounding by indication, depression severity, and potential exposure misclassification.

Exposure to SSRIs, particularly later in pregnancy, may have an increased risk for PPHN. PPHN occurs in 1-2 per 1000 live births in the general population and is associated with substantial neonatal morbidity and mortality.

Animal Data

Reproduction studies were performed at doses up to 50 mg/kg/day in rats and 6 mg/kg/day in rabbits administered during organogenesis. These doses are approximately 8 (rat) and less than 2 (rabbit) times the maximum recommended human dose (MRHD – 60 mg) on an mg/m^2 basis. These studies have revealed no evidence of developmental effects. However, in rats, there was an increase in pup deaths during the first 4 days of lactation when dosing occurred during the last trimester of gestation and continued throughout lactation. This effect occurred at a dose of 1 mg/kg/day which is less than the MRHD on an mg/m^2 basis. The no effect dose for rat pup mortality was not determined. The cause of these deaths is not known.

8.2 Lactation

Risk Summary

Data from the published literature report the presence of paroxetine in human milk (see Data). There are reports of agitation, irritability, poor feeding and poor weight gain in infants exposed to paroxetine through breast milk (see Clinical Considerations). There are no data on the effect of paroxetine on milk production. The developmental and health benefits of breastfeeding should be considered along with the mother’s clinical need for Paxil and any potential adverse effects on the breastfed child from Paxil or from underlying maternal condition.

Clinical Considerations

Infants exposed to PAXIL should be monitored for agitation, irritability, poor feeding and poor weight gain.

Data

Published literature suggests the presence of paroxetine in human milk with relative infant doses ranging between 0.4% to 2.2%, and a milk/plasma ratio of <1. No significant amounts were detected in the plasma of infants after breastfeeding.

8.3 Females and Males of Reproductive Potential

Infertility

Male

Based on findings from clinical studies, paroxetine may affect sperm quality which may impair fertility; it is not known if this effect is reversible [see Nonclinical Toxicology (13.1)].

8.4 Pediatric Use

The safety and effectiveness of PAXIL in pediatric patients have not been established [see Box Warning]. Effectiveness was not demonstrated in three placebo-controlled trials in 752 PAXIL-treated pediatric patients with MDD.

Antidepressants increase the risk of suicidal thoughts and behaviors in pediatric patients [see Boxed Warning, Warnings and Precautions (5.1)]. Decreased appetite and weight loss have been observed in association with the use of SSRIs.

In placebo-controlled clinical trials conducted with pediatric patients, the following adverse reactions were reported in at least 2% of pediatric patients treated with PAXIL and occurred at a rate at least twice that for pediatric patients receiving placebo: emotional lability (including self-harm, suicidal thoughts, attempted suicide, crying, and mood fluctuations), hostility, decreased appetite, tremor, sweating, hyperkinesia, and agitation.

Adverse reactions upon discontinuation of treatment with PAXIL in the pediatric clinical trials that included a taper phase regimen, which occurred in at least 2% of patients and at a rate at least twice that of placebo, were: emotional lability (including suicidal ideation, suicide attempt, mood changes, and tearfulness), nervousness, dizziness, nausea, and abdominal pain .

8.5 Geriatric Use

In premarketing clinical trials with PAXIL, 17% of patients treated with PAXIL (approximately 700) were 65 years of age or older. Pharmacokinetic studies revealed a decreased clearance in the elderly, and a lower starting dose is recommended;, however, no overall differences in safety or effectiveness were observed between elderly and younger patients [see Dosage and Administration (2.4), Clinical Pharmacology (12.3)].

SSRIs including PAXIL, have been associated with cases of clinically significant hyponatremia in elderly patients, who may be at greater risk for this adverse reaction [see Warnings and Precautions (5.7)].

8.6 Renal and Hepatic Impairment

Increased plasma concentrations of paroxetine occur in patients with renal and hepatic impairment. The initial dosage of PAXIL should be reduced in patients with severe renal impairment and in patients with severe hepatic impairment [see Dosage and Administration (2.4), Clinical Pharmacology (12.3)].

10 OVERDOSAGE

The following have been reported with paroxetine tablet overdosage:

- Seizures, which may be delayed, and altered mental status including coma.
- Cardiovascular toxicity, which may be delayed, including QRS and QTc interval prolongation. Hypertension most commonly seen, but rarely can see hypotension alone or with co-ingestants including alcohol.
- Serotonin syndrome (patients with a multiple drug overdosage with other proserotonergic drugs may have a higher risk).

Gastrointestinal decontamination with activated charcoal should be considered in patients who present early after a paroxetine overdose.

Consider contacting a poison center (1-800-222-1222) or a medical toxicologist for additional overdosage management recommendations.

11 DESCRIPTION

PAXIL contains paroxetine hydrochloride, an SSRI. It is the hydrochloride salt of a phenylpiperidine compound identified chemically as (-)-trans-4R-(4'-fluorophenyl)-3S-[(3',4'-methylenedioxyphenoxy) methyl] piperidine hydrochloride hemihydrate and has the empirical formula of C19H20FNO3·HCl·1/2H2O. The molecular weight is 374.8 (329.4 as free base). The structural formula of paroxetine hydrochloride is:

Paroxetine hydrochloride is an odorless, off‑white powder, having a melting point range of 120° to 138°C and a solubility of 5.4 mg/mL in water.

PAXIL Tablets

PAXIL tablets are for oral administration. Each film‑coated tablet contains 10 mg, 20 mg, 30 mg, or 40 mg of paroxetine equivalent to 11.1 mg, 22.2 mg, 33.3 mg or 44.4 mg of paroxetine hydrochloride, respectively.

Inactive ingredients consist of dibasic calcium phosphate dihydrate, hypromellose, magnesium stearate, polyethylene glycols, polysorbate 80, sodium starch glycolate, titanium dioxide, and 1 or more of the following: D&C Red No. 30 aluminum lake, D&C Yellow No. 10 aluminum lake, FD&C Blue No. 2 aluminum lake, FD&C Yellow No. 6 aluminum lake.

PAXIL Oral Suspension

PAXIL oral suspension is for oral administration. Each 5 mL contains 10 mg of paroxetine equivalent to 11.1 mg of paroxetine hydrochloride.

The oral suspension is not currently marketed.

Inactive ingredients consist of citric acid (anhydrous), FD&C yellow No. 6, flavorings, glycerin, methylparaben, microcrystalline cellulose and carboxymethylcellulose sodium, polacrilin potassium, propylene glycol, propylparaben, purified water, saccharin sodium, simethicone emulsion and sodium citrate (dihydrate).

12 CLINICAL PHARMACOLOGY

12.1 Mechanism of Action

The mechanism of action of PAXIL in the treatment of MDD, SAD, OCD, PD, GAD, and PTSD is unknown, but is presumed to be linked to potentiation of serotonergic activity in the central nervous system resulting from inhibition of neuronal reuptake of serotonin (5‑hydroxy‑tryptamine, 5‑HT).

12.2 Pharmacodynamics

Studies at clinically relevant doses in humans have demonstrated that paroxetine blocks the uptake of serotonin into human platelets. In vitro studies in animals also suggest that paroxetine is a potent and highly selective inhibitor of neuronal serotonin reuptake (SSRI) and has only very weak effects on norepinephrine and dopamine neuronal reuptake.

12.3 Pharmacokinetics

Nonlinearity in pharmacokinetics is observed with increasing doses of PAXIL.

In a meta-analysis of paroxetine from 4 studies done in healthy volunteers following multiple dosing of 20 mg/day to 40 mg/day, males did not exhibit a significantly lower Cmax or AUC than females.

Absorption

Paroxetine hydrochloride is completely absorbed after oral dosing of a solution of the hydrochloride salt. In a study in which normal male subjects (n = 15) received 30 mg tablets daily for 30 days, steady‑state paroxetine concentrations were achieved by approximately 10 days for most subjects, although it may take substantially longer in an occasional patient. At steady state, mean values of Cmax, Tmax, Cmin, and T½ were 61.7 ng/mL (CV 45%), 5.2 hr. (CV 10%), 30.7 ng/mL (CV 67%), and 21 hours (CV 32%), respectively. The steady‑state Cmax and Cmin values were about 6 and 14 times what would be predicted from single‑dose studies. Steady‑state drug exposure based on AUC0-24 was about 8 times greater than would have been predicted from single-dose data in these subjects. The excess accumulation is a consequence of the fact that 1 of the enzymes that metabolizes paroxetine is readily saturable.

Paroxetine is equally bioavailable from the oral suspension and tablet.

Effect of Food

The effects of food on the bioavailability of paroxetine were studied in subjects administered a single dose with and without food. AUC was only slightly increased (6%) when drug was administered with food but the Cmax was 29% greater, while the time to reach peak plasma concentration decreased from 6.4 hours post‑dosing to 4.9 hours.

Distribution

Paroxetine distributes throughout the body, including the CNS, with only 1% remaining in the plasma.

Approximately 95% and 93% of paroxetine is bound to plasma protein at 100 ng/mL and 400 ng/mL, respectively. Under clinical conditions, paroxetine concentrations would normally be less than 400 ng/mL. Paroxetine does not alter the in vitro protein binding of phenytoin or warfarin.

Elimination

Metabolism

The mean elimination half-life is approximately 21 hours (CV 32%) after oral dosing of 30 mg tablets daily for 30 days of PAXIL.

In steady‑state dose proportionality studies involving elderly and nonelderly patients, at doses of 20 mg to 40 mg daily for the elderly and 20 mg to 50 mg daily for the nonelderly, some nonlinearity was observed in both populations, again reflecting a saturable metabolic pathway. In comparison to Cmin values after 20 mg daily, values after 40 mg daily were only about 2 to 3 times greater than doubled.

Paroxetine is extensively metabolized after oral administration. The principal metabolites are polar and conjugated products of oxidation and methylation, which are readily cleared. Conjugates with glucuronic acid and sulfate predominate, and major metabolites have been isolated and identified. Data indicate that the metabolites have no more than 1/50 the potency of the parent compound at inhibiting serotonin uptake. The metabolism of paroxetine is accomplished in part by CYP2D6. Saturation of this enzyme at clinical doses appears to account for the nonlinearity of paroxetine kinetics with increasing dose and increasing duration of treatment. The role of this enzyme in paroxetine metabolism also suggests potential drug‑drug interactions [see Drug Interactions (7)]. Pharmacokinetic behavior of paroxetine has not been evaluated in subjects who are deficient in CYP2D6 (poor metabolizers).

Excretion

Approximately 64% of a 30-mg oral solution dose of paroxetine was excreted in the urine with 2% as the parent compound and 62% as metabolites over a 10‑day post‑dosing period. About 36% was excreted in the feces (probably via the bile), mostly as metabolites and less than 1% as the parent compound over the 10‑day post‑dosing period.

Drug Interaction Studies

There are clinically significant, known drug interactions between paroxetine and other drugs [see Drug Interactions (7)].

Figure 1. Impact of Paroxetine on the Pharmacokinetics of Co-Administered Drugs (log scale)

Figure 2. Impact of Co-Administered Drugs on the Pharmacokinetics of Paroxetine

Theophylline: Reports of elevated theophylline levels associated with PAXIL treatment have been reported. While this interaction has not been formally studied, it is recommended that theophylline levels be monitored when these drugs are concurrently administered.

Drugs Metabolized by Cytochrome CYP3A4

An in vivo interaction study involving the coadministration under steady-state conditions of paroxetine and terfenadine, a substrate for CYP3A4, revealed no effect of paroxetine on terfenadine pharmacokinetics. In addition, in vitro studies have shown ketoconazole, a potent inhibitor of CYP3A4 activity, to be at least 100 times more potent than paroxetine as an inhibitor of the metabolism of several substrates for this enzyme, including terfenadine, triazolam, and cyclosporine. Paroxetine’s extent of inhibition of CYP3A4 activity is not expected to be of clinical significance.

Specific Populations

The impact of specific populations on the pharmacokinetics of paroxetine are shown in Figure 3.

The recommended starting dosage and maximum dosage of PAXIL is reduced in elderly patients, patients with severe renal impairment, and patients with severe hepatic impairment [see Dosage and Administration (2.4)].

Figure 3. Impact of Specific Population on the Pharmacokinetics of Paroxetine (log scale)

13 NONCLINICAL TOXICOLOGY

13.1 Carcinogenesis, Mutagenesis, Impairment of Fertility

Carcinogenesis

Two‑year carcinogenicity studies were conducted in rodents given paroxetine in the diet at 1, 5, and 25 mg/kg/day (mice) and 1, 5, and 20 mg/kg/day (rats). These doses are up to 2 (mouse) and 3 (rat) times the MRHD of 60 mg on a mg/m^2 basis. There was a significantly greater number of male rats in the high‑dose group with reticulum cell sarcomas (1/100, 0/50, 0/50, and 4/50 for control, low-, middle-, and high‑dose groups, respectively) and a significantly increased linear trend across dose groups for the occurrence of lymphoreticular tumors in male rats. Female rats were not affected. Although there was a dose‑related increase in the number of tumors in mice, there was no drug-related increase in the number of mice with tumors. The relevance of these findings to humans is unknown.

Mutagenesis

Paroxetine produced no genotoxic effects in a battery of 5 in vitro and 2 in vivo assays that included the following: Bacterial mutation assay, mouse lymphoma mutation assay, unscheduled DNA synthesis assay, and tests for cytogenetic aberrations in vivo in mouse bone marrow and in vitro in human lymphocytes and in a dominant lethal test in rats.

Impairment of Fertility

A reduced pregnancy rate was found in reproduction studies in rats at a dose of paroxetine of 15 mg/kg/day, which is 2 times the MRHD of 60 mg on a mg/m^2 basis. Irreversible lesions occurred in the reproductive tract of male rats after dosing in toxicity studies for 2 to 52 weeks. These lesions consisted of vacuolation of epididymal tubular epithelium at 50 mg/kg/day and atrophic changes in the seminiferous tubules of the testes with arrested spermatogenesis at 25 mg/kg/day (8 and 4 times the MRHD of 60 mg on a mg/m^2 basis).

14 CLINICAL STUDIES

14.1 Major Depressive Disorder

The efficacy of PAXIL as a treatment for major depressive disorder (MDD) has been established in 6 placebo‑controlled studies of patients with MDD (aged 18 to 73). In these studies, PAXIL was shown to be statistically significantly more effective than placebo in treating MDD by at least 2 of the following measures: Hamilton Depression Rating Scale (HDRS), the Hamilton depressed mood item, and the Clinical Global Impression (CGI)‑Severity of Illness. PAXIL was statistically significantly better than placebo in improvement of the HDRS sub‑factor scores, including the depressed mood item, sleep disturbance factor, and anxiety factor.

Long-term efficacy of PAXIL for treatment of MDD in outpatients was demonstrated in a randomized withdrawal study. Patients who responded to PAXIL (HDRS total score <8) during an initial 8-week open-label treatment phase were then randomized to continue PAXIL or placebo, for up to 1 year. Patients treated with PAXIL demonstrated a statistically significant lower relapse rate during the withdrawal phase (15%) compared to those on placebo (39%). Effectiveness was similar for male and female patients.

14.2 Obsessive Compulsive Disorder

The effectiveness of PAXIL in the treatment of obsessive compulsive disorder (OCD) was demonstrated in two 12‑week multicenter placebo-controlled studies of adult outpatients (Studies 1 and 2). Patients had moderate to severe OCD (DSM‑IIIR) with mean baseline ratings on the Yale Brown Obsessive Compulsive Scale (YBOCS) total score ranging from 23 to 26. In study 1, a dose-range finding study, patients received fixed daily doses of PAXIL 20 mg, 40 mg, or 60 mg. Study 1 demonstrated that daily doses of PAXIL 40 mg and 60 mg are effective in the treatment of OCD. Patients receiving doses of PAXIL 40 mg and 60 mg experienced a mean reduction of approximately 6 and 7 points, respectively, on the YBOCS total score which was statistically significantly greater than the approximate 4-point reduction at 20 mg and a 3-point reduction in the placebo‑treated patients. Study 2 was a flexible-dose study comparing PAXIL 20 mg to 60 mg daily with clomipramine 25 mg to 250 mg daily or placebo). In this study, patients receiving PAXIL experienced a mean reduction of approximately 7 points on the YBOCS total score, which was statistically significantly greater than the mean reduction of approximately 4 points in placebo‑treated patients.

The following table provides the outcome classification by treatment group on Global Improvement items of the Clinical Global Impression (CGI) scale for Study 1.

Table 10: Outcome Classification (%) on CGI-Global Improvement Item for Completers in Study 1 in Patients with OCD

Outcome Classification | Placebo (n = 74) % | PAXIL 20 mg (n = 75) % | PAXIL 40 mg (n = 66) % | PAXIL 60 mg (n = 66) %
Worse | 14 | 7 | 7 | 3
No Change | 44 | 35 | 22 | 19
Minimally Improved | 24 | 33 | 29 | 34
Much Improved | 11 | 18 | 22 | 24
Very Much Improved | 7 | 7 | 20 | 20

Subgroup analyses did not indicate that there were any differences in treatment outcomes as a function of age or gender.

The long‑term efficacy of PAXIL for the treatment of OCD was established in a long‑term extension to Study 1. Patients who responded to PAXIL during the 3‑month double‑blind phase and a 6‑month extension on open‑label PAXIL 20 mg to 60 mg daily were randomized to either PAXIL or placebo in a 6‑month double‑blind relapse prevention phase. Patients randomized to PAXIL were statistically significantly less likely to relapse than placebo-treated patients.

14.3 Panic Disorder

The effectiveness of PAXIL in the treatment of panic disorder (PD) was demonstrated in three 10- to 12‑week multicenter, placebo‑controlled studies of adult outpatients (Studies 1, 2, and 3). Patients had PD (DSM-IIIR), with or without agoraphobia. In these studies, PAXIL was shown to be statistically significantly more effective than placebo in treating PD by at least 2 out of 3 measures of panic attack frequency and on the Clinical Global Impression Severity of Illness score.

Study 1 was a 10‑week dose‑range finding study; patients received fixed doses of PAXIL 10 mg, 20 mg, or 40 mg daily or placebo. A statistically significant difference from placebo was observed only for the PAXIL 40 mg daily group. At endpoint, 76% of patients receiving PAXIL 40 mg daily were free of panic attacks, compared to 44% of placebo‑treated patients.

Study 2 was a 12‑week flexible‑dose study comparing PAXIL 10 mg to 60 mg daily and placebo. At endpoint, 51% of PAXIL-treated patients were free of panic attacks compared to 32% of placebo‑treated patients.

Study 3 was a 12‑week flexible‑dose study comparing PAXIL 10 mg to 60 mg daily to placebo in patients concurrently receiving standardized cognitive behavioral therapy. At endpoint, 33% of the PAXIL‑treated patients showed a reduction to 0 or 1 panic attacks compared to 14% of placebo-treated patients.

In Studies 2 and 3, the mean PAXIL dose for completers at endpoint was approximately 40 mg daily.

Long‑term efficacy of PAXIL in PD was demonstrated in an extension to Study 1. Patients who responded to PAXIL during the 10‑week double‑blind phase and during a 3‑month double‑blind extension phase were randomized to either PAXIL 10 mg, 20 mg, or 40 mg daily or placebo in a 3‑month double‑blind relapse prevention phase. Patients randomized to PAXIL were statistically significantly less likely to relapse than placebo-treated patients.

Subgroup analyses did not indicate that there were any differences in treatment outcomes as a function of age or gender.

14.4 Social Anxiety Disorder

The effectiveness of PAXIL in the treatment of social anxiety disorder (SAD) was demonstrated in three 12‑week, multicenter, placebo‑controlled studies (Studies 1, 2, and 3) of adult outpatients with SAD (DSM‑IV). In these studies, the effectiveness of PAXIL compared to placebo was evaluated on the basis of (1) the proportion of responders, as defined by a Clinical Global Impression (CGI) Improvement score of 1 (very much improved) or 2 (much improved), and (2) change from baseline in the Liebowitz Social Anxiety Scale (LSAS).

Studies 1 and 2 were flexible-dose studies comparing PAXIL 20 mg to 50 mg daily and placebo. PAXIL demonstrated statistically significant superiority over placebo on both the CGI Improvement responder criterion and the Liebowitz Social Anxiety Scale (LSAS). In Study 1, for patients who completed to week 12, 69% of PAXIL‑treated patients compared to 29% of placebo‑treated patients were CGI Improvement responders. In Study 2, CGI Improvement responders were 77% and 42% for the PAXIL- and placebo‑treated patients, respectively.

Study 3 was a 12‑week study comparing fixed doses of PAXIL 20 mg, 40 mg, or 60 mg daily with placebo. PAXIL 20 mg was statistically significantly superior to placebo on both the LSAS Total Score and the CGI Improvement responder criterion; there were trends for superiority over placebo for the PAXIL 40 mg and 60 mg daily dose groups. There was no indication in this study of any additional benefit for doses higher than 20 mg daily.

Subgroup analyses generally did not indicate differences in treatment outcomes as a function of age, race, or gender.

14.5 Generalized Anxiety Disorder

The effectiveness of PAXIL in the treatment of generalized anxiety disorder (GAD) was demonstrated in two 8‑week, multicenter, placebo‑controlled studies (Studies 1 and 2) of adult outpatients with GAD (DSM‑IV).

Study 1 was an 8‑week study comparing fixed doses of PAXIL 20 mg or 40 mg daily with placebo. Doses of PAXIL 20 mg or 40 mg were both demonstrated to be statistically significantly superior to placebo on the Hamilton Rating Scale for Anxiety (HAM‑A) total score.

There was not sufficient evidence in this study to suggest a greater benefit for the PAXIL 40 mg daily dose compared to the 20 mg daily dose.

Study 2 was a flexible‑dose study comparing PAXIL 20 mg to 50 mg daily and placebo. PAXIL demonstrated statistically significant superiority over placebo on the Hamilton Rating Scale for Anxiety (HAM‑A) total score.

A third study, a flexible-dose study comparing PAXIL 20 mg to 50 mg daily to placebo, did not demonstrate statistically significant superiority of PAXIL over placebo on the Hamilton Rating Scale for Anxiety (HAM‑A) total score, the primary outcome.

Subgroup analyses did not indicate differences in treatment outcomes as a function of race or gender. There were insufficient elderly patients to conduct subgroup analyses on the basis of age.

In a long-term trial, 566 patients meeting DSM-IV criteria for GAD, who had responded during a single-blind, 8-week acute treatment phase with PAXIL 20 mg to 50 mg daily, were randomized to continuation of PAXIL at their same dose, or to placebo, for up to 24 weeks of observation for relapse. Response during the single-blind phase was defined by having a decrease of ≥2 points compared to baseline on the CGI-Severity of Illness scale, to a score of ≤3. Relapse during the double-blind phase was defined as an increase of ≥2 points compared to baseline on the CGI-Severity of Illness scale to a score of ≥4, or withdrawal due to lack of efficacy. Patients continuing to receive PAXIL experienced a statistically significantly lower relapse rate over the subsequent 24 weeks compared to those receiving placebo.

14.6 Posttraumatic Stress Disorder

The effectiveness of PAXIL in the treatment of Posttraumatic Stress Disorder (PTSD) was demonstrated in two 12-week, multicenter, placebo-controlled studies (Studies 1 and 2) of adult outpatients who met DSM-IV criteria for PTSD. The mean duration of PTSD symptoms for the 2 studies combined was 13 years (ranging from 0.1 year to 57 years). The percentage of patients with secondary MDD or non-PTSD anxiety disorders in the combined 2 studies was 41% (356 out of 858 patients) and 40% (345 out of 858 patients), respectively. Study outcome was assessed by (1) the Clinician-Administered PTSD Scale Part 2 (CAPS-2) score and (2) the Clinical Global Impression-Global Improvement Scale (CGI-I). The CAPS-2 is a multi-item instrument that measures 3 aspects of PTSD with the following symptom clusters: Reexperiencing/intrusion, avoidance/numbing and hyperarousal. The 2 primary outcomes for each trial were (1) change from baseline to endpoint on the CAPS-2 total score (17 items), and (2) proportion of responders on the CGI-I, where responders were defined as patients having a score of 1 (very much improved) or 2 (much improved).

Study 1 was a 12-week study comparing fixed doses of PAXIL 20 mg or 40 mg daily to placebo. Doses of PAXIL 20 mg and 40 mg were demonstrated to be statistically significantly superior to placebo on change from baseline for the CAPS-2 total score and on proportion of responders on the CGI-I. There was not sufficient evidence in this study to suggest a greater benefit for the 40 mg daily dose compared to the 20 mg daily dose.

Study 2 was a 12-week flexible-dose study comparing PAXIL 20 mg to 50 mg daily to placebo. PAXIL was demonstrated to be significantly superior to placebo on change from baseline for the CAPS-2 total score and on proportion of responders on the CGI-I.

A third study, a flexible-dose study comparing PAXIL 20 mg to 50 mg daily to placebo, demonstrated PAXIL to be statistically significantly superior to placebo on change from baseline for CAPS-2 total score, but not on proportion of responders on the CGI-I.

The majority of patients in these trials were women (68% women: 377 out of 551 subjects in Study 1 and 66% women: 202 out of 303 subjects in Study 2). Subgroup analyses did not indicate differences in treatment outcomes as a function of gender. There were an insufficient number of patients who were 65 years and older or were non-Caucasian to conduct subgroup analyses on the basis of age or race, respectively.

16 HOW SUPPLIED/STORAGE AND HANDLING

PAXIL (paroxetine) tablets are oval shaped tablets supplied as:

Tablet Strength | Color | Engraved Descriptors | Package Configuration | NDC Number
10 mg | yellow | Scored, “PAXIL” on front and “10” on back | Bottles of 30 | NDC 60505-4517-3
20 mg | pink | Scored, “PAXIL” on front and “20” on back | Bottles of 30 | NDC 60505-4518-3
30 mg | blue | “PAXIL” on front and “30” on back | Bottles of 30 | NDC 60505-4519-3
40 mg | green | “PAXIL” on front and “40” on back | Bottles of 30 | NDC 60505-4520-3

Store tablets between 15° and 30°C (59° and 86°F).

PAXIL (paroxetine) oral suspension is supplied as:

Strength | Color/Flavor | Package Configuration | NDC Number
10 mg/5 mL | Orange/orange | Bottles containing 250 mL | NDC 60505-0402-5

Store suspension at or below 25°C (77°F). The oral suspension is not currently marketed.

17 PATIENT COUNSELING INFORMATION

Advise the patient to read the FDA-approved patient labeling (Medication Guide).

Suicidal Thoughts and Behaviors

Advise patients and caregivers to look for the emergence of suicidality, especially early during treatment and when the dosage is adjusted up or down, and instruct them to report such symptoms to the healthcare provider [see Boxed Warning and Warnings and Precautions (5.1)].

Serotonin Syndrome

Caution patients about the risk of serotonin syndrome, particularly with the concomitant use of PAXIL with other serotonergic drugs including triptans, tricyclic antidepressants, opioids, lithium, tryptophan, buspirone, amphetamines, St. John’s Wort, and with drugs that impair metabolism of serotonin (in particular, MAOIs, both those intended to treat psychiatric disorders and also others, such as linezolid). Instruct patients to contact their health care provider or report to the emergency room if they experience signs or symptoms of serotonin syndrome [see Warnings and Precautions (5.2), Drug Interactions (7)].

Concomitant Medications

Advise patients to inform their physician if they are taking, or plan to take, any prescription or over-the-counter drugs, since there is a potential for drug-drug interactions [see Warning and Precautions (5.3), Drug Interactions (7)].

Increased Risk of Bleeding

Inform patients about the concomitant use of PAXIL with aspirin, NSAIDs, other antiplatelet drugs, warfarin, or other anticoagulants because the combined use has been associated with an increased risk of bleeding. Advise patients to inform their health care providers if they are taking or planning to take any prescription or over-the counter medications that increase the risk of bleeding [see Warnings and Precautions (5.5)].

Activation of Mania/Hypomania

Advise patients and their caregivers to observe for signs of activation of mania/hypomania and instruct them to report such symptoms to the healthcare provider [see Warnings and Precautions (5.6)].

Discontinuation Syndrome

Advise patients not to abruptly discontinue PAXIL and to discuss any tapering regimen with their healthcare provider. Inform patients that adverse reactions can occur when PAXIL is discontinued [See Warnings and Precautions (5.7)].

Sexual Dysfunction

Advise patients that use of PAXIL may cause symptoms of sexual dysfunction in both male and female patients. Inform patients that they should discuss any changes in sexual function and potential management strategies with their healthcare provider [see Warnings and Precautions (5.13)].

Administration Information for Oral Suspension

Instruct patients to shake the oral suspension well before administration [see Dosage and Administration (2.1)].

Allergic Reactions

Advise patients to notify their healthcare provider if they develop an allergic reaction such as rash, hives, swelling, or difficulty breathing [see Adverse Reactions (6.1, 6.2)].

Embryo-Fetal Toxicity

Advise women to notify their healthcare provider if they become pregnant or intend to become pregnant during treatment with PAXIL. Advise women of risks associated with first trimester use of PAXIL and that use later in pregnancy may lead to an increased risk for neonatal complications requiring prolonged hospitalization, respiratory support, tube feeding, and/or persistent pulmonary hypertension of the newborn (PPHN) [see Warnings and Precautions (5.4), Use in Specific Populations (8.1)]. Advise women that there is a pregnancy exposure registry that monitors pregnancy outcomes in women exposed to PAXIL during pregnancy [see Warnings and Precautions (5.4), Use in Specific Populations (8.1)].

Lactation

Advise breastfeeding women using PAXIL to monitor infants for agitation, irritability, poor feeding, and poor weight gain and to seek medical care if they notice these signs [see Use in Specific Populations (8.2)].

Females and Males of Reproductive Potential

Advise men that PAXIL may affect sperm quality, which may impair fertility; it is not known if this effect is reversible [see Use in Specific Populations (8.3)].

Manufactured by: Apotex Inc. Toronto, Ontario M9L 1T9

Manufactured for: Apotex Corp., Weston, Florida USA 33326

PAXIL® are registered trademarks of the GlaxoSmithKline group of companies.

All registered trademarks in this document are the property of their respective owners

Medication Guide

PAXIL® (PAX-il)

(paroxetine)

tablets

oral suspension

What is the most important information I should know about PAXIL?

PAXIL can cause serious side effects, including:

- Increased risk of suicidal thoughts or actions. PAXIL and other antidepressant medicines may increase suicidal thoughts and actions in some people 24 years of age and younger, especially within the first few months of treatment or when the dose is changed. PAXIL is not for use in children.

  - Depression or other mental illnesses are the most important causes of suicidal thoughts and actions.

How can I watch for and try to prevent suicidal thoughts and actions?

- Pay close attention to any changes, especially sudden changes in mood, behavior, thoughts or feelings or if you develop suicidal thoughts or actions. This is very important when an antidepressant medicine is started or when the does is changed.
- Call your healthcare provider right away to report new or sudden changes in mood, behavior, thoughts or feelings or if you develop suicidal thoughts or actions.
- Keep all follow-up visits with your healthcare provider as scheduled. Call your healthcare provider between visits as needed, especially if you have concerns about symptoms.

Call your healthcare provider or get emergency medical help right away if you have any of the following symptoms, especially if they are new, worse, or worry you:

- attempts to commit suicide
- acting aggressive or violent
- new or worse depression
- feeling agitated, restless, angry, or irritable
- an increase in activity and talking more than what is normal for you
- acting on dangerous impulses
- thoughts about suicide or dying
- new or worse anxiety or panic attacks
- trouble sleeping
- other unusual changes in behavior or mood

What is PAXIL?

PAXIL is a prescription medicine used in adults to treat:

- A certain type of depression called Major Depressive Disorder (MDD)
- Obsessive Compulsive Disorder (OCD)
- Panic Disorder (PD)
- Social Anxiety Disorder (SAD)
- Generalized Anxiety Disorder (GAD)
- Posttraumatic Stress Disorder (PTSD)

Do not take PAXIL if you:

- take a monoamine oxidase inhibitor (MAOI)
- have stopped taking an MAOI in the last 14 days
- are being treated with the antibiotic linezolid or the intravenous methylene blue
- are taking pimozide
- are taking thioridazine
- are allergic to paroxetine or any of the ingredients in PAXIL. See the end of this Medication Guide for a complete list of ingredients in PAXIL.

Ask your healthcare provider or pharmacist if you are not sure if you take an MAOI or one of these medicines, including the antibiotic linezolid or intravenous methylene blue.

Do not start taking an MAOI for at least 14 days after you stop treatment with PAXIL.

Before taking PAXIL, tell your healthcare provider about all your medical conditions, including if you:

- have heart problems
- have or had bleeding problems
- have, or have a family history of, bipolar disorder, mania or hypomania
- have or had seizures or convulsions
- have glaucoma (high pressure in the eye)
- have low sodium levels in your blood
- have bone problems
- have kidney or liver problems
- are pregnant or plan to become pregnant. PAXIL may harm your unborn baby.
  - Taking PAXIL during your first trimester of pregnancy may cause your baby to be at an increased risk of having a heart problem (cardiac malformations) at birth.
  - Taking PAXIL during your third trimester of pregnancy may cause your baby to have breathing, temperature, and feeding problems, low muscle tone, and irritability after birth and may cause your baby to be at an increased risk of a serious lung problem at birth. Talk to your healthcare provider about the risk to your unborn baby if you take PAXIL during pregnancy.
  - Tell your healthcare provider right away if you become pregnant or think you are pregnant during treatment with PAXIL.
  - There is a pregnancy registry for females who are exposed to PAXIL during pregnancy. The purpose of the registry is to collect information about the health of females exposed to PAXIL and their baby. If you become pregnant during treatment with PAXIL talk to your healthcare provider about registering with the National Pregnancy Registry for Antidepressants at 1-866-961-2388 or visit online at https://womensmentalhealth.org/clinical-and-research-programs/pregnancyregistry/antidepressants/.
- are breastfeeding or plan to breastfeed. PAXIL passes into your breast milk. Talk to your healthcare provider about the best way to feed your baby during treatment with PAXIL.

Tell your healthcare provider about all the medicines you take, including prescription and over-the-counter medicines, vitamins, and herbal supplements.

PAXIL and some other medicines may affect each other causing possible serious side effects. PAXIL may affect the way other medicines work and other medicines may affect the way PAXIL works.

Especially tell your healthcare provider if you take:

- medicines used to treat migraine headaches called triptans
- tricyclic antidepressants
- lithium
- tramadol, fentanyl, meperidine, methadone, or other opioids
- tryptophan
- buspirone
- amphetamines
- St. John’s Wort
- medicines that can affect blood clotting such as aspirin, nonsteroidal anti-inflammatory drugs (NSAIDs), warfarin
- diuretics
- tamoxifen
- medicines used to treat mood, anxiety, psychotic, or thought disorders, including selective serotonin reuptake (SSRIs) and serotonin norepinephrine reuptake inhibitors (SNRIs)

Ask your healthcare provider if you are not sure if you are taking any of these medicines. Your healthcare provider can tell you if it is safe to take PAXIL with your other medicines.

Do not start or stop any other medicines during treatment with PAXIL without talking to your healthcare provider first. Stopping PAXIL suddenly may cause you to have serious side effects. See, “What are the possible side effects of PAXIL?”

Know the medicines you take. Keep a list of them to show to your healthcare provider and pharmacist when you get a new medicine.

How should I take PAXIL?

- Take PAXIL exactly as prescribed. Your healthcare provider may need to change the dose of PAXIL until it is the right dose for you.
- Take PAXIL 1 time each day in the morning.
- PAXIL may be taken with or without food.
- If you are taking PAXIL oral suspension, shake the suspension well before taking.
- If you take too much PAXIL, call your poison control center at 1-800-222-1222 or go to the nearest hospital emergency room right away.

What are possible side effects of PAXIL?

PAXIL can cause serious side effects, including:

- See, “What is the most important information I should know about PAXIL?”
- Serotonin syndrome. A potentially life-threatening problem called serotonin syndrome can happen when you take PAXIL with certain other medicines. See, “Who should not take PAXIL?” Call your healthcare provider or go to the nearest hospital emergency room right away if you have any of the following signs and symptoms of serotonin syndrome:
  - agitation
  - seeing or hearing things that are not real (hallucinations)
  - confusion
  - coma
  - fast heart beat
  - changes in blood pressure
  - dizziness
  - sweating
  - flushing
  - high body temperature (hyperthermia)
  - shaking (tremors), stiff muscles, or muscle twitching
  - loss of coordination
  - seizures
  - nausea, vomiting, diarrhea
- Eye problems (angle-closure glaucoma). PAXIL may cause a type of eye problem called angle-closure glaucoma in people with certain other eye conditions. You may want to undergo an eye examination to see if you are at risk and receive preventative treatment if you are. Call your healthcare provider if you have eye pain, changes in your vision, or swelling or redness in or around the eye.
- Medicine interactions. Taking PAXIL with certain other medicines including thioridazine and pimozide may increase the risk of developing a serious heart problem called QT prolongation.
- Seizures (convulsions).
- Manic episodes. Manic episodes may happen in people with bipolar disorder who take PAXIL. Symptoms may include:
  - greatly increased energy
  - racing thoughts
  - unusually grand ideas
  - talking more or faster than usual
  - severe problems sleeping
  - reckless behavior
  - excessive happiness or irritability
- Discontinuation syndrome. Suddenly stopping PAXIL may cause you to have serious side effects. Your healthcare provider may want to decrease your dose slowly. Symptoms may include:
  - nausea
  - sweating
  - changes in your mood
  - irritability and agitation
  - dizziness
  - electric shock feeling (paresthesia)
  - tremor
  - anxiety
  - confusion
  - headache
  - tiredness
  - problems sleeping
  - hypomania
  - ringing in your ears (tinnitus)
  - seizures
- Low sodium levels in your blood (hyponatremia). Low sodium levels in your blood that may be serious and may cause death, can happen during treatment with PAXIL. Elderly people and people who take certain medicines may be at a greater risk for developing low sodium levels in your blood. Signs and symptoms may include:
  - headache
  - difficulty concentrating
  - memory changes
  - confusion
  - weakness and unsteadiness on your feet which can lead to falls

In more severe or more sudden cases, signs and symptoms include:

- seeing or hearing things that are not real (hallucinations)
- fainting
- seizures
- coma
- stopping breathing (respiratory arrest)
- Abnormal bleeding. Taking PAXIL with aspirin, NSAIDs, or blood thinners may increase this risk. Tell your healthcare provider about any unusual bleeding or bruising.
- Bone fractures.
- Sexual problems (dysfunction). Taking selective serotonin reuptake inhibitors (SSRIs), including PAXIL, may cause sexual problems.

Symptoms in males may include:

- Delayed ejaculation or inability to have an ejaculation
- Decreased sex drive
- Problems getting or keeping an erection

Symptoms in females may include:

- Decreased sex drive
- Delayed orgasm or inability to have an orgasm

Talk to your healthcare provider if you develop any changes in your sexual function or if you have any questions or concerns about sexual problems during treatment with PAXIL. There may be treatments your healthcare provider can suggest.

The most common side effects of PAXIL include:

- male and female sexual function problems
- constipation
- diarrhea
- dry mouth
- problems sleeping
- nervousness
- sweating
- yawning
- weakness (asthenia)
- decreased appetite
- dizziness
- infection
- nausea
- sleepiness
- shaking (tremor)

These are not all the possible side effects of PAXIL.

Call your doctor for medical advice about side effects. You may report side effects to FDA at 1-800-FDA-1088.

How should I store PAXIL?

- Store PAXIL tablets between 59ºF to 86ºF (15ºC to 30ºC).
- Store PAXIL oral suspension at or below 77ºF (25ºC).

Keep PAXIL and all medicines out of the reach of children.

General information about the safe and effective use of PAXIL.

Medicines are sometimes prescribed for purposes other than those listed in a Medication Guide. Do not take PAXIL for a condition for which it was not prescribed. Do not give PAXIL to other people, even if they have the same symptoms that you have. It may harm them. You may ask your healthcare provider or pharmacist for information about PAXIL that is written for healthcare professionals.

What are the ingredients in PAXIL?

Active ingredient: paroxetine hydrochloride

Inactive ingredients:

Tablets: dibasic calcium phosphate dihydrate, hypromellose, magnesium stearate, polyethylene glycols, polysorbate 80, sodium starch glycolate, titanium dioxide, and 1 or more of the following: D&C Red No. 30 aluminum lake, D&C Yellow No. 10 aluminum lake, FD&C Blue No. 2 aluminum lake, FD&C Yellow No. 6 aluminum lake

Oral suspension: citric acid (anhydrous), FD&C yellow No. 6, flavorings, glycerin, methylparaben, microcrystalline cellulose and carboxymethylcellulose sodium, polacrilin potassium, propylene glycol, propylparaben, purified water, saccharin sodium, simethicone emulsion and sodium citrate (dihydrate)

Manufactured by: Apotex Inc.,Toronto, Ontario, Canada M9L 1T9

Manufactured for: Apotex Corp.: Weston, Florida USA 33326

PAXIL® and PAXIL CR® are registered trademarks of the GlaxoSmithKline group of companies.

All other registered trademarks are the property of their respective owners.

For more information about PAXIL call 1-800-706-5575.

This Medication Guide has been approved by the U.S. Food and Drug Administration.

Revised: 11/2024

PACKAGE LABEL

NDC 60505-4517-3

PAXIL®

PAROXETINE HCl TABLETS

10 mg

30 Tablets

Scored Tablets

Federal Law requires dispensing of Paxil® with the Medication Guide provided with this bottle.

Rx only

Store tablets between 15o and 30oC (59o and 86oF). Dispense in a tight, light-resistant container.

Each tablet contains paroxetine hydrochloride equivalent to 10 mg paroxetine.

Dosage: See accompanying prescribing information.

Important: Use safety closures when dispensing this product unless otherwise directed by physician or requested by purchaser.

Manufactured by:

Apotex Inc.

Toronto, Ontario

Canada M9L 1T9

Manufactured for:

Apotex Corp.

Weston, Florida 33326

PACKAGE LABEL

NDC 60505-4518-3

PAXIL®

PAROXETINE HCl TABLETS

20 mg

30 Tablets

Federal Law requires dispensing of Paxil® with the Medication Guide provided with this bottle.

Rx only

Store tablets between 15o and 30oC (59o and 86oF). Dispense in a tight, light-resistant container.

Each tablet contains paroxetine hydrochloride equivalent to 20 mg paroxetine.

Dosage: See accompanying prescribing information.

Important: Use safety closures when dispensing this product unless otherwise directed by physician or requested by purchaser.

Manufactured by:

Apotex Inc.

Toronto, Ontario

Canada M9L 1T9

Manufactured for:

Apotex Corp.

Weston, Florida 33326

PACKAGE LABEL

NDC 60505-4519-3

PAXIL®

PAROXETINE HCl TABLETS

30 mg

30 Tablets

Federal Law requires dispensing of Paxil® with the Medication Guide provided with this bottle.

Rx only

Store tablets between 15o and 30oC (59o and 86oF). Dispense in a tight, light-resistant container.

Each tablet contains paroxetine hydrochloride equivalent to 30 mg paroxetine.

Dosage: See accompanying prescribing information.

Important: Use safety closures when dispensing this product unless otherwise directed by physician or requested by purchaser.

Manufactured by:

Apotex Inc.

Toronto, Ontario

Canada M9L 1T9

Manufactured for:

Apotex Corp.

Weston, Florida 33326

PACKAGE LABEL

NDC 60505-4520-3

PAXIL®

PAROXETINE HCl TABLETS

40 mg

30 Tablets

Federal Law requires dispensing of Paxil® with the Medication Guide provided with this bottle.

Rx only

Store tablets between 15o and 30oC (59o and 86oF). Dispense in a tight, light-resistant container.

Each tablet contains paroxetine hydrochloride equivalent to 40 mg paroxetine.

Dosage: See accompanying prescribing information.

Important: Use safety closures when dispensing this product unless otherwise directed by physician or requested by purchaser.

Manufactured by:

Apotex Inc.

Toronto, Ontario

Canada M9L 1T9

Manufactured for:

Apotex Corp.

Weston, Florida 33326